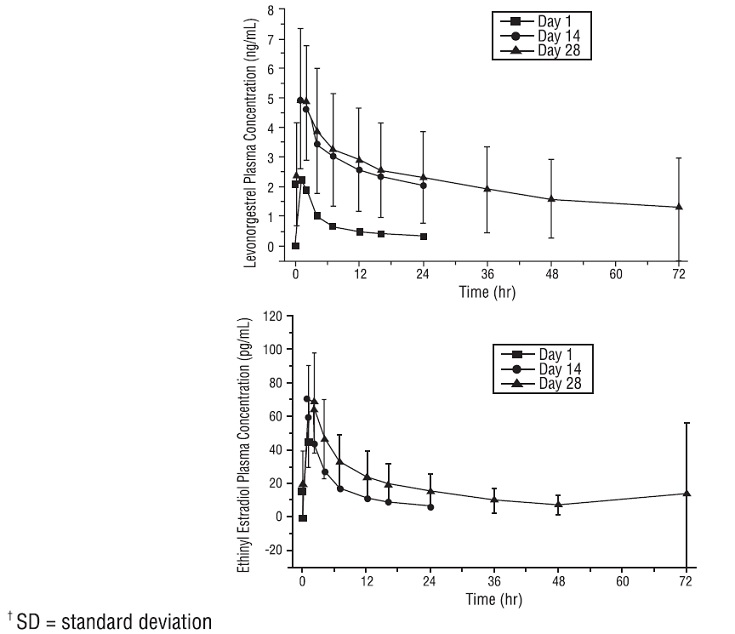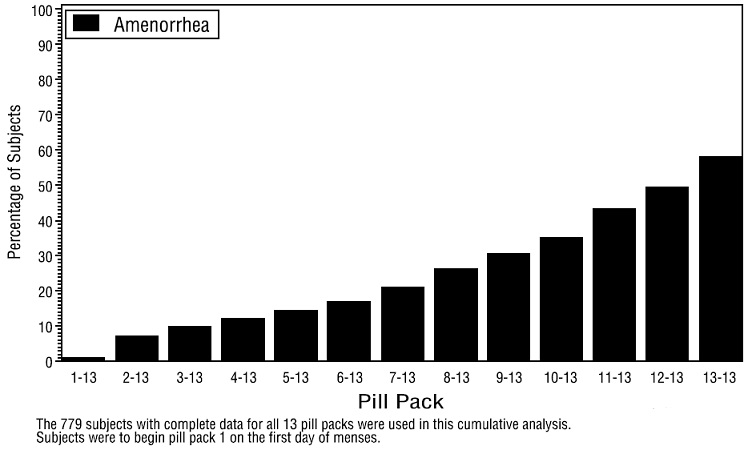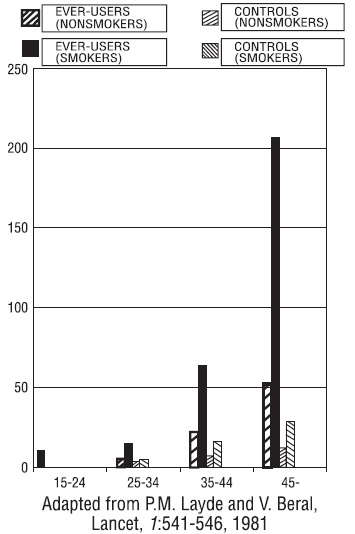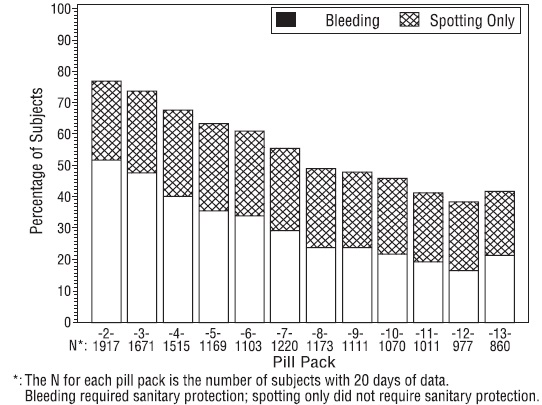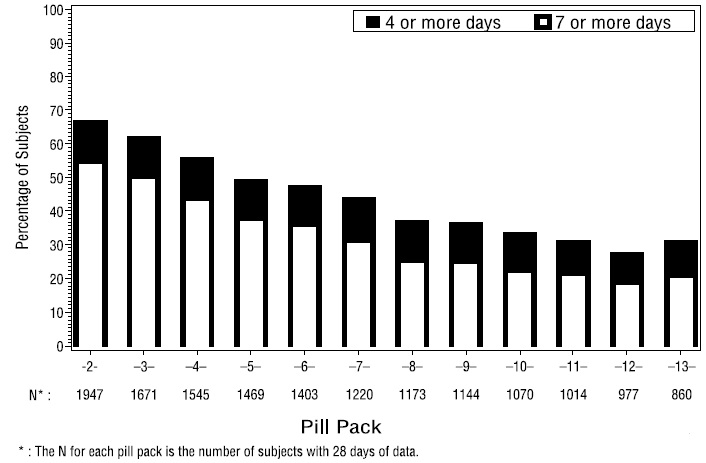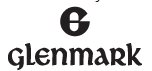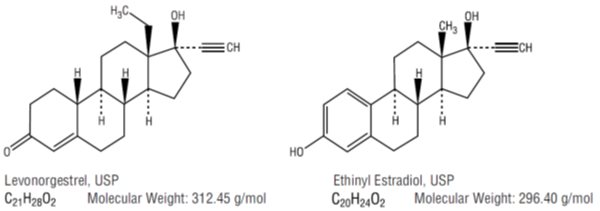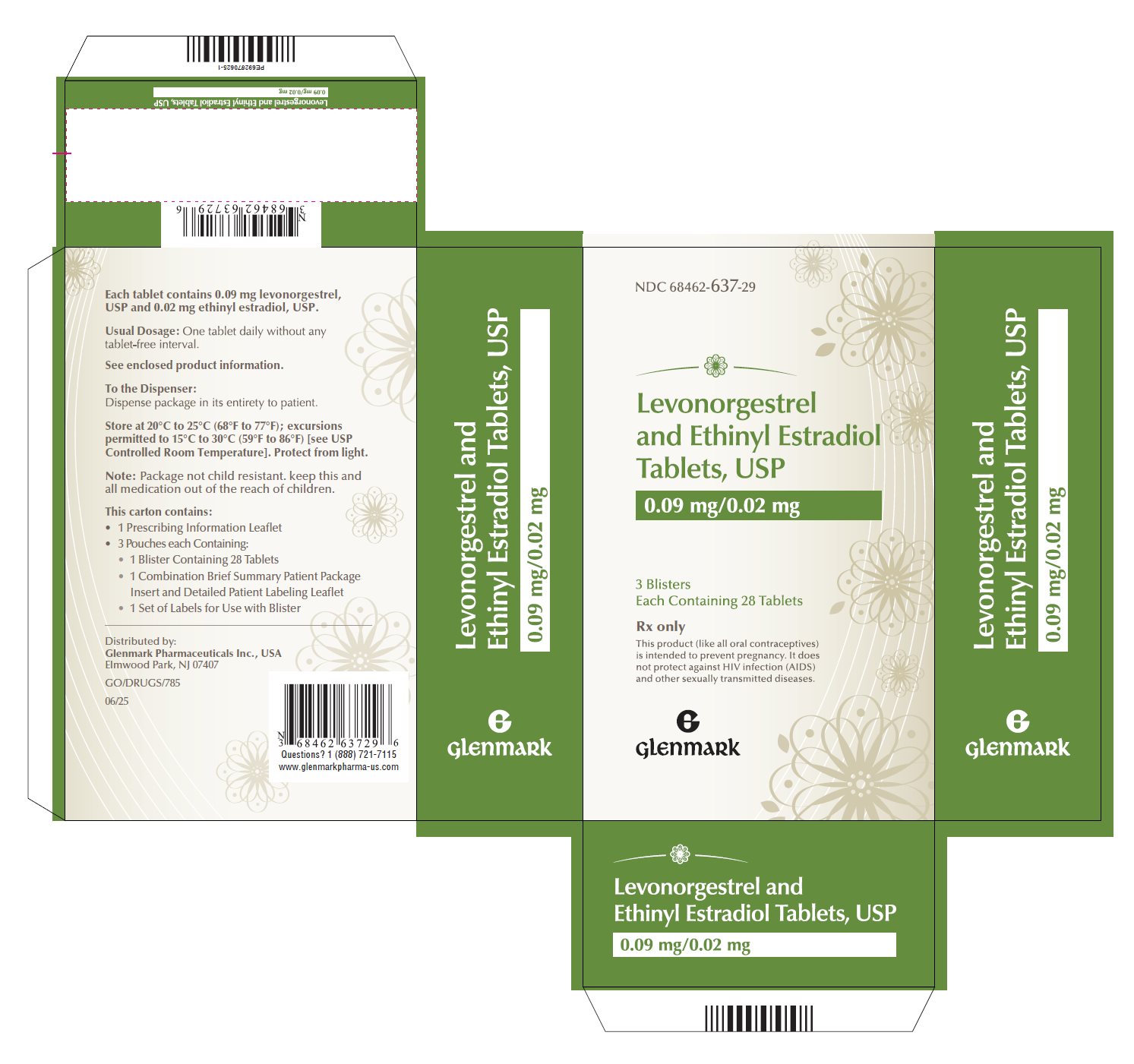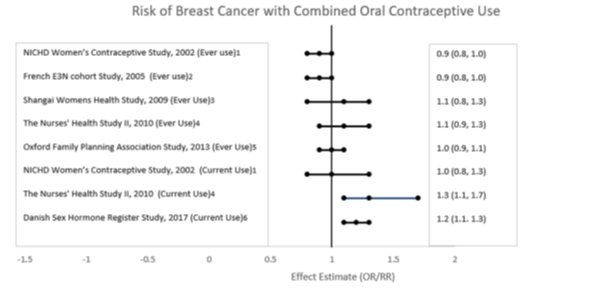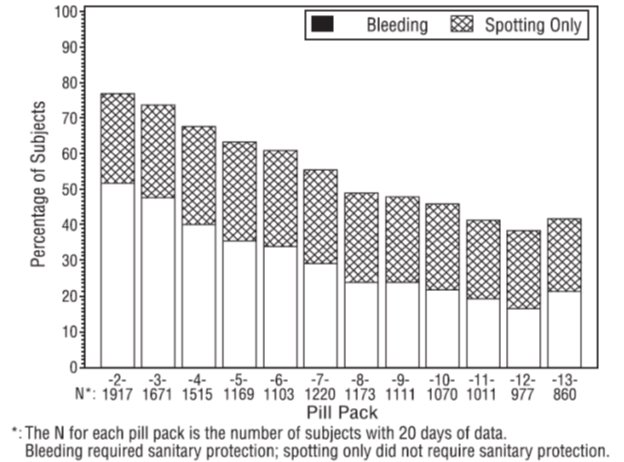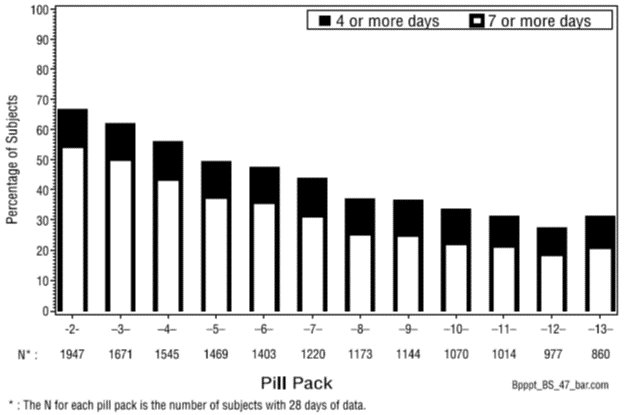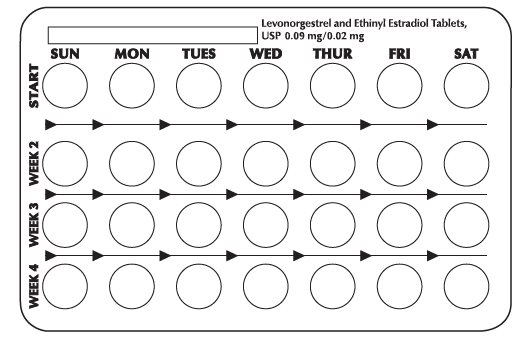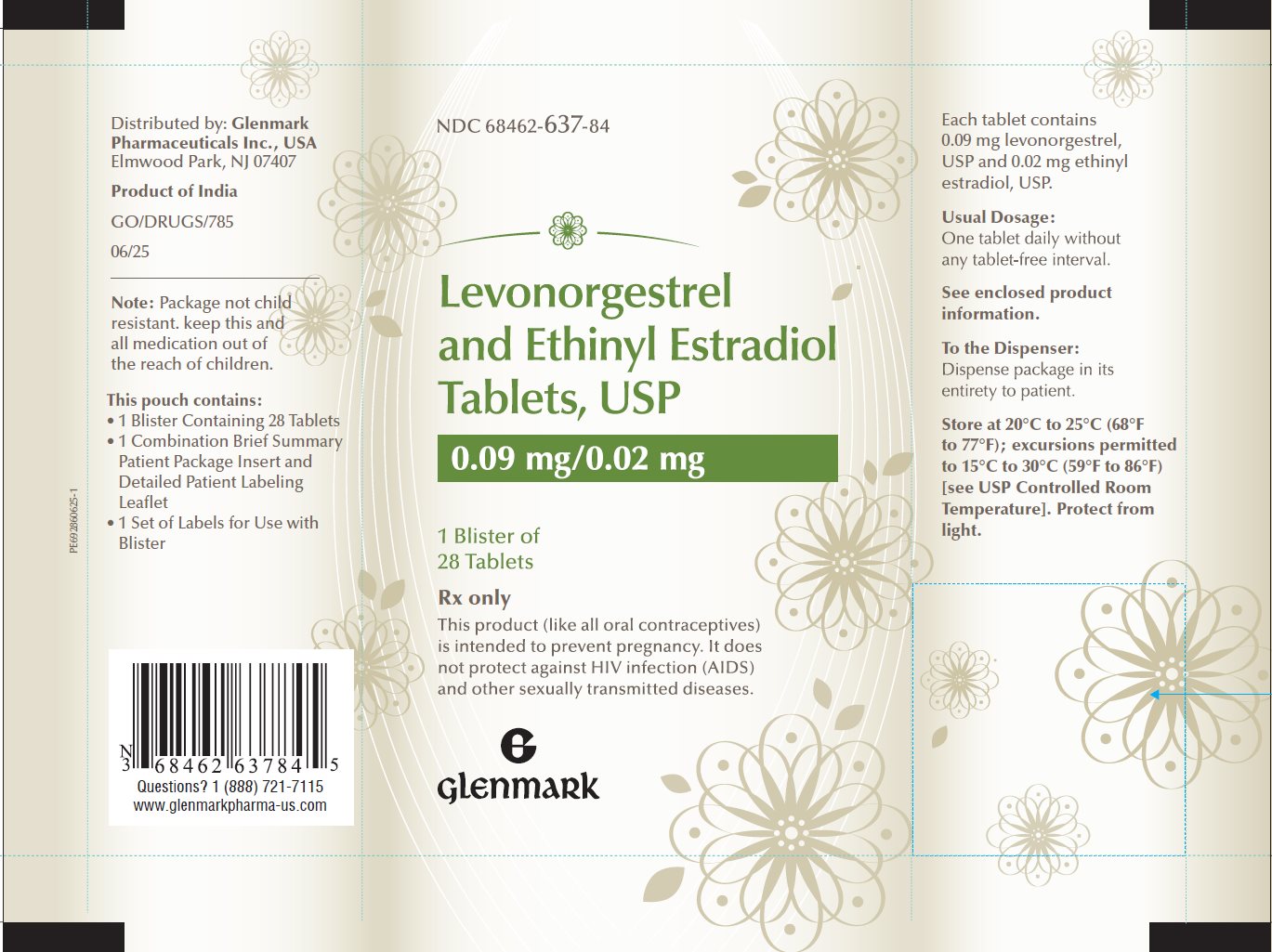 DRUG LABEL: Levonorgestrel and Ethinyl Estradiol
NDC: 68462-637 | Form: TABLET
Manufacturer: Glenmark Pharmaceuticals Inc., USA
Category: prescription | Type: HUMAN PRESCRIPTION DRUG LABEL
Date: 20260130

ACTIVE INGREDIENTS: LEVONORGESTREL 90 ug/1 1; ETHINYL ESTRADIOL 20 ug/1 1
INACTIVE INGREDIENTS: LACTOSE MONOHYDRATE; MAGNESIUM STEARATE; MICROCRYSTALLINE CELLULOSE; POVIDONE, UNSPECIFIED; POLACRILIN POTASSIUM; TALC; TITANIUM DIOXIDE; POLYETHYLENE GLYCOL, UNSPECIFIED; FERRIC OXIDE RED; FERRIC OXIDE YELLOW; HYPROMELLOSE, UNSPECIFIED

Levonorgestrel and Ethinyl Estradiol Tablets, USP
0.09 mg/0.02 mg

Rx only

Patients should be counseled that oral contraceptives do not protect against transmission of HIV (AIDS) and other sexually transmitted diseases (STDs) such as chlamydia, genital herpes, genital warts, gonorrhea, hepatitis B, and syphilis.

DESCRIPTION

Twenty-eight (28) brownish peach to light brown tablets each containing 0.09 mg of levonorgestrel, USP (18, 19-Dinorpregn-4-en-20-yn-3-one, 13-ethyl-17-hydroxy-, (17α)-(-) (-)-13-Ethyl –hydroxy-18, 19 dinor-17α-pregn-4-en-20-yn-3-one, and 0.02 mg of ethinyl estradiol, USP, 19-Nor-17α-pregna-1,3,5(10)-trien-20-yne-3,17-diol. The inactive ingredients present are lactose monohydrate, magnesium stearate, microcrystalline cellulose, povidone, polacrilin potassium, talc, hypromellose, titanium dioxide, polyethylene glycol, iron oxide red and iron oxide yellow.

CLINICAL PHARMACOLOGY

Mode of Action

Combination oral contraceptives act by suppression of gonadotropins. Although the primary mechanism of this action is inhibition of ovulation, other alterations include changes in the cervical mucus (which increase the difficulty of sperm entry into the uterus) and the endometrium (which reduce the likelihood of implantation).

Pharmacokinetics

Absorption

No specific investigation of the absolute bioavailability of levonorgestrel and ethinyl estradiol in humans has been conducted. However, literature indicates that levonorgestrel is rapidly and completely absorbed after oral administration (bioavailability about 100%) and is not subject to first-pass metabolism. Ethinyl estradiol is rapidly and almost completely absorbed from the gastrointestinal tract but, due to first-pass metabolism in gut mucosa and liver, the bioavailability of ethinyl estradiol is between 38% and 48%.

A summary of the single dose and multiple dose levonorgestrel and ethinyl estradiol pharmacokinetic parameters for 18 women under fasting conditions is provided in Table 1. The plasma concentrations of levonorgestrel and ethinyl estradiol reached steady-state by approximately day 14. Levonorgestrel and ethinyl estradiol concentrations did not increase from days 14 to 28, but did increase from days 1 to 28.

Table 1: Mean (SD) Pharmacokinetic Parameters of Levonorgestrel and ethinyl estradiol Over a 28-Day Dosing Period
LNG
Day | Cmax (ng/mL) | Tmax (h) | t1/2 (h) | AUC0-24 (ng•h/mL)
1 | 2.4 (0.9) | 1.2 (0.4) | - | 16 (8)
14 | 5.4 (2.1) | 1.7 (1.4) | - | 68 (36)
28 | 5.7 (2.1) | 1.3 (0.8) | 36 (19) | 74 (41)
EE
Day | (pg/mL) | (h) | (h) | (pg•h/mL)
1 | 47.7 (20.1) | 1.3 (0.5) | - | 378 (140)
14 | 72.7 (37.2) | 1.4 (0.5) | - | 695 (361)
28 | 74.4 (29.7) | 1.4 (0.5) | 21 (7) | 717 (351)

The mean plasma concentrations of levonorgestrel and ethinyl estradiol following single (day 1) and multiple (days 14 and 28) oral administrations of levonorgestrel 0.09 mg in combination with ethinyl estradiol 0.02 mg to 18 healthy women is provided in Figure 1.

Figure 1: Mean Plasma ± SD† Concentrations of Levonorgestrel and Ethinyl Estradiol Following Single (Day 1) and Multiple (Days 14 and 28) Oral Administrations of Levonorgestrel 0.09 mg in Combination with Ethinyl Estradiol 0.02 mg to Healthy Women

The effect of food on the rate and the extent of levonorgestrel and ethinyl estradiol absorption following oral administration of levonorgestrel and ethinyl estradiol has not been evaluated.

Distribution

Levonorgestrel in serum is primarily bound to sex hormone-binding globulin (SHBG). Ethinyl estradiol is about 97% bound to serum albumin. Ethinyl estradiol does not bind to SHBG, but induces SHBG synthesis.

Metabolism

Levonorgestrel: The most important metabolic pathways are reduction of the Δ4-3-oxo group and hydroxylation at positions 2α, 1β, and 16β, followed by conjugation. Most of the circulating metabolites are sulfates of 3α, 5β-tetrahydro-levonorgestrel, while excretion occurs predominantly in the form of glucuronides. Some of the parent levonorgestrel also circulates as 17β-sulfate. Metabolic clearance rates may differ among individuals by several-fold, and this may account in part for the wide variation observed in levonorgestrel concentrations among users.

Ethinyl estradiol: Cytochrome P450 enzymes (CYP3A4) in the liver are responsible for the 2–hydroxylation that is the major oxidative reaction. The 2-hydroxy metabolite is further transformed by methylation, sulfation, and glucuronidation prior to urinary and fecal excretion. Levels of CYP3A4 vary widely among individuals and can explain the variation in rates of ethinyl estradiol 2-hydroxylation.

Excretion

The terminal elimination half-life for levonorgestrel in levonorgestrel and ethinyl estradiol is about 36 hours. Levonorgestrel and its metabolites are excreted in the urine (40% to 68%) and in feces (16% to 48%). The terminal elimination half-life of ethinyl estradiol in levonorgestrel and ethinyl estradiol is about 21 hours.

Ethinyl estradiol is excreted in the urine and feces as glucuronide and sulfate conjugates and undergoes enterohepatic recirculation.

Special Populations

Race

No formal studies on the effect of race on the pharmacokinetic parameters of levonorgestrel and ethinyl estradiol were conducted.

Hepatic Insufficiency

No formal studies have evaluated the effect of hepatic disease on the disposition of levonorgestrel and ethinyl estradiol. However, steroid hormones may be poorly metabolized in patients with impaired liver function.

Renal Insufficiency

No formal studies have evaluated the effect of renal disease on the disposition of levonorgestrel and ethinyl estradiol.

Drug-Drug Interactions

See PRECAUTIONS section - Drug Interactions.

INDICATIONS AND USAGE

Levonorgestrel and ethinyl estradiol tablets are indicated for the prevention of pregnancy in women who elect to use oral contraceptives as a method of contraception.

Oral contraceptives are highly effective for pregnancy prevention. Table 2 lists the typical unintended pregnancy rates for users of combination oral contraceptives and other methods of contraception. The efficacy of these contraceptive methods, except sterilization, the IUD, and implants, depend upon the reliability with which they are used. Correct and consistent use of methods can result in lower failure rates.

Table 2: Percentage of Women Experiencing an Unintended Pregnancy During The First Year of Typical Use and The First Year of Perfect Use of Contraception and The Percentage Continuing Use at The End of the First Year. United States.
 | % of Women Experiencing an Unintended Pregnancy within the First Year of Use |  | % of Women Continuing Use at One Year^3
Method (1) | Typical Use^1 (2) | Perfect Use^2 (3) | (4)
Chance^4 | 85 | 85
Spermicides^5 | 26 | 6 | 40
Periodic abstinence | 25 |  | 63
Calendar |  | 9
Ovulation Method |  | 3
Sympto-Thermal^6 |  | 2
Post-Ovulation |  | 1
Cap^7
Parous Women | 40 | 26 | 42
Nulliparous Women | 20 | 9 | 56
Sponge
Parous Women | 40 | 20 | 42
Nulliparous Women | 20 | 9 | 56
Diaphragm^7 | 20 | 6 | 56
Withdrawal | 19 | 4
Condom^8
Female (RealityTM) | 21 | 5 | 56
Male | 14 | 3 | 61
Pill | 5 |  | 71
Progestin only |  | 0.5
Combined |  | 0.1
IUD
Progesterone T | 2 | 1.5 | 81
Copper T380A | 0.8 | 0.6 | 78
LNg 20 | 0.1 | 0.1 | 81
Depo-Provera® | 0.3 | 0.3 | 70
Levonorgestrel Implants (Norplant®) | 0.05 | 0.05 | 88
Female Sterilization | 0.5 | 0.5 | 100
Male Sterilization | 0.15 | 0.10 | 100

Emergency Contraceptive Pills: The FDA has concluded that certain combined oral contraceptives containing ethinyl estradiol and norgestrel or levonorgestrel are safe and effective for use as postcoital emergency contraception. Treatment initiated within 72 hours after unprotected intercourse reduces the risk of pregnancy by at least 75%.^9

Lactation Amenorrhea Method: LAM is a highly effective, temporary method of contraception.^10

Source: Trussell J. Contraceptive efficacy. In: Hatcher RA, Trussell J, Stewart F, Cates W, Stewart GK, Kowel D, Guest F. Contraceptive Technology: Seventeenth Revised Edition. New York NY: Irvington Publishers; 1998.

1. Among typical couples who initiate use of a method (not necessarily for the first time), the percentage who experience an accidental pregnancy during the first year if they do not stop use for any other reason.
2. Among couples who initiate use of a method (not necessarily for the first time) and who use it perfectly (both consistently and correctly), the percentage who experience an accidental pregnancy during the first year if they do not stop use for any other reason.
3. Among couples attempting to avoid pregnancy, the percentage who continue to use a method for one year.
4. The percents becoming pregnant in columns (2) and (3) are based on data from populations where contraception is not used and from women who cease using contraception in order to become pregnant. Among such populations, about 89% become pregnant within one year. This estimate was lowered slightly (to 85%) to represent the percent who would become pregnant within one year among women now relying on reversible methods of contraception if they abandoned contraception altogether.
5. Foams, creams, gels, vaginal suppositories, and vaginal film.
6. Cervical mucus (ovulation) method supplemented by calendar in the pre-ovulatory and basal body temperature in the post-ovulatory phases.
7. With spermicidal cream or jelly.
8. Without spermicides.
9. The treatment schedule is one dose within 72 hours after unprotected intercourse and a second dose 12 hours after the first dose. The FDA has declared the following dosage regimens of oral contraceptives to be safe and effective for emergency contraception: for tablets containing 0.05 mg of ethinyl estradiol and 0.5 mg of norgestrel 1 dose is 2 tablets; for tablets containing 0.02 mg of ethinyl estradiol and 0.1 mg of levonorgestrel 1 dose is 5 tablets; for tablets containing 0.03 mg of ethinyl estradiol and 0.15 mg of levonorgestrel 1 dose is 4 tablets.
10. However, to maintain effective protection against pregnancy, another method of contraception must be used as soon as menstruation resumes, the frequency or duration of breastfeeds is reduced, bottle feeds are introduced, or the baby reaches 6 months of age.

Clinical Studies

The efficacy and safety of levonorgestrel and ethinyl estradiol were studied in 2 one-year clinical trials of subjects age 18 to 49. There were no exclusions for body mass index (BMI), weight, or bleeding history.

The primary efficacy and safety study (313-NA) was a one-year open-label clinical trial that treated 2,134 subjects in North America. Of these subjects 1,213 (56.8%) discontinued prematurely, including 102 (4.8%) discontinued by the Sponsor for early study closure. The mean weight of subjects in this study was 70.38 kg. The efficacy of levonorgestrel and ethinyl estradiol was assessed by the number of pregnancies that occurred after the onset of treatment and within 14 days of the last dose. Among subjects 35 years or less, there were 23 pregnancies (4 of these occurred during the interval 1 to 14 days after the last day of pill use) during 12,572 28-day pill packs of use. The resulting total Pearl Index was 2.38 (95% CI: 1.51, 3.57) and the one-year life table pregnancy rate was 2.39 (95% CI: 1.57, 3.62). Pill pack cycles during which subjects used back-up contraception or were not sexually active were not included in these calculations. Among women 35 years or less who took the pills completely as directed, there were 15 pregnancies (method failures) resulting in a Pearl Index of 1.55 (95% CI: 0.87, 2.56) and the one-year life table pregnancy rate was 1.59 (95% CI: 0.95 to 2.67).

In a second supportive study conducted in Europe (315-EU), 641 subjects were randomized to levonorgestrel and ethinyl estradiol (n=323) or the cyclic comparator of 0.1 mg levonorgestrel and 0.02 mg ethinyl estradiol (n=318). The mean weight of subjects in this study was 63.86 kg. The efficacy analysis among women 35 years or less included 2,756 levonorgestrel and ethinyl estradiol pill packs and 2,886 cyclic comparator pill packs. There was one pregnancy in the levonorgestrel and ethinyl estradiol group that occurred within 14 days following the last dose. There were three pregnancies in the cyclic comparator group.

Inhibition of Menses (Bleeding Profile)

The bleeding profile for subjects in Study 313-NA also was assessed. Women with a history of unscheduled bleeding and/or spotting were not excluded from the study.

In those subjects who provided complete bleeding data, the percentage of patients who were amenorrheic in a given cycle and remained amenorrheic through cycle 13 (cumulative amenorrhea rate) was determined (Figure 2).

Figure 2: Percentage of Subjects with Cumulative Amenorrhea for Each Pill Pack through Pill Pack 13

When prescribing levonorgestrel and ethinyl estradiol, the convenience of having no scheduled menstrual bleeding should be weighed against the inconvenience of unscheduled bleeding and spotting (see WARNINGS, 11).

CONTRAINDICATIONS

Levonorgestrel and ethinyl estradiol tablets are contraindicated in females who are known to have or develop the following conditions :

Thrombophlebitis or thromboembolic disorders

History of deep-vein thrombophlebitis or thromboembolic disorders

Cerebrovascular or coronary artery disease (current or past history)

Valvular heart disease with thrombogenic complications

Thrombogenic rhythm disorders

Hereditary or acquired thrombophilias

Major surgery with prolonged immobilization

Diabetes with vascular involvement

Headaches with focal neurological symptoms such as aura

Uncontrolled hypertension

Current diagnosis of, or history of, breast cancer, which may be hormone-sensitive

Carcinoma of the endometrium or other known or suspected estrogen-dependent neoplasia

Undiagnosed abnormal genital bleeding

Cholestatic jaundice of pregnancy or jaundice with prior pill use

Hepatic adenomas or carcinomas, or active liver disease

Known or suspected pregnancy

Hypersensitivity to any of the components of levonorgestrel and ethinyl estradiol.

Are receiving Hepatitis C drug combinations containing ombitasvir/paritaprevir/ritonavir, with or without dasabuvir, due to the potential for ALT elevations (see Warnings, RISK OF LIVER ENZYME ELEVATIONS WITH CONCOMITANT HEPATITIS C TREATMENT).

WARNINGS

Cigarette smoking increases the risk of serious cardiovascular side effects from oral contraceptive use. This risk increases with age and with the extent of smoking (in epidemiologic studies, 15 or more cigarettes per day was associated with a significantly increased risk) and is quite marked in women over 35 years of age. Women who use oral contraceptives should be strongly advised not to smoke.

The use of oral contraceptives is associated with increased risks of several serious conditions including venous and arterial thrombotic and thromboembolic events (such as myocardial infarction, thromboembolism, stroke, and transient ischemic attack), hepatic neoplasia, gallbladder disease, and hypertension, although the risk of serious morbidity or mortality is very small in healthy women without underlying risk factors. The risk of morbidity and mortality increases significantly in the presence of other underlying risk factors such as certain inherited or acquired thrombophilias, hypertension, hyperlipidemias, obesity, diabetes, and surgery or trauma with increased risk of thrombosis (see CONTRAINDICATIONS).

Practitioners prescribing oral contraceptives should be familiar with the following information relating to these risks.

The information contained in this package insert is principally based on studies carried out in patients who used oral contraceptives with higher doses of estrogens and progestogens than those in common use today. The effect of long-term use of the oral contraceptives with lower doses of both estrogens and progestogens remains to be determined.

Throughout this labeling, epidemiological studies reported are of two types: retrospective or case control studies and prospective or cohort studies. Case control studies provide a measure of the relative risk of disease, namely, a ratio of the incidence of a disease among oral contraceptive users to that among nonusers. The relative risk does not provide information on the actual clinical occurrence of a disease. Cohort studies provide a measure of attributable risk, which is the difference in the incidence of disease between oral contraceptive users and nonusers. The attributable risk does provide information about the actual occurrence of a disease in the population. For further information, the reader is referred to a text on epidemiological methods.

1. Thromboembolic Disorders and Other Vascular Problems

Levonorgestrel and ethinyl estradiol is a non-cyclic oral contraceptive that provides a low daily dose of estrogen and progestin; however, levonorgestrel and ethinyl estradiol provides women with more hormonal exposure on a yearly basis (13 additional weeks of hormone intake per year) than conventional cyclic oral contraceptives containing the same strength of synthetic estrogens and similar strength of progestins.

a. Myocardial Infarction

An increased risk of myocardial infarction has been attributed to oral contraceptive use. This risk is primarily in smokers or women with other underlying risk factors for coronary-artery disease such as hypertension, hypercholesterolemia, morbid obesity, and diabetes. The relative risk of heart attack for current oral contraceptive users has been estimated to be two to six. The risk is very low under the age of 30.

Smoking in combination with oral contraceptive use has been shown to contribute substantially to the incidence of myocardial infarction in women in their mid-thirties or older with smoking accounting for the majority of excess cases. Mortality rates associated with circulatory disease have been shown to increase substantially in smokers over the age of 35 and nonsmokers over the age of 40 (Figure 3) among women who use oral contraceptives.

Figure 3: Circulatory Disease Mortality Rates per 100,000 Woman Years by Age, Smoking Status and Oral Contraceptive Use

Oral contraceptives may compound the effects of well-known risk factors, such as hypertension, diabetes, hyperlipidemias, age, and obesity. In particular, some progestogens are known to decrease HDL cholesterol and cause glucose intolerance, while estrogens may create a state of hyperinsulinism. Oral contraceptives have been shown to increase blood pressure among users (see section 9in WARNINGS). Similar effects on risk factors have been associated with an increased risk of heart disease. Oral contraceptives must be used with caution in women with cardiovascular disease risk factors.

b. Venous Thrombosis and Thromboembolism

An increased risk of venous thromboembolic and thrombotic disease associated with the use of oral contraceptives is well established. The risk of venous thrombotic and thromboembolic events is further increased in women with conditions predisposing for venous thrombosis and thromboembolism. Case control studies have found the relative risk of users compared to non-users to be 3 for the first episode of superficial venous thrombosis, 4 to 11 for deep-vein thrombosis or pulmonary embolism, and 1.5 to 6 for women with predisposing conditions for venous thromboembolic disease. Cohort studies have shown the relative risk to be somewhat lower, about 3 for new cases and about 4.5 for new cases requiring hospitalization. The approximate incidence of deep-vein thrombosis and pulmonary embolism in users of low dose (<0.05 mg ethinyl estradiol) combination oral contraceptives is up to 4 per 10,000 woman-years compared to 0.5 to 3 per 10,000 woman-years for non-users. However, the incidence is less than that associated with pregnancy (6 per 10,000 woman-years). The excess risk is highest during the first year a woman ever uses a combined oral contraceptive. Venous thromboembolism may be fatal. The risk of thromboembolic disease due to oral contraceptives is not related to length of use and gradually disappears after pill use is stopped.

A post-marketing observational study evaluated the risk of venous thromboembolism with levonorgestrel and ethinyl estradiol use in two large US automated healthcare claims databases. The study was not completed as planned due to low accrual of levonorgestrel and ethinyl estradiol users in these databases and discontinuation of the product from the market due to low usage. At study discontinuation, the crude incidence rate of venous thromboembolism among levonorgestrel and ethinyl estradiol users (n=12,281) was 17.6 per 10,000 person-years, compared to 8.8 per 10,000 person-years among the users of cyclic oral contraceptives containing 20 mcg of ethinyl estradiol and a progestogen, and 5.1 per 10,000 person-years among the users of cyclic oral contraceptives containing the progestin levonorgestrel and 20 mcg of ethinyl estradiol. Adjustment for important risk factors or confounders (such as obesity, cardiovascular disease and other diseases) for venous thromboembolism could not be performed due to the small sample size. Although the study results suggest an elevated risk of venous thromboembolism with current levonorgestrel and ethinyl estradiol use compared to cyclic oral hormonal contraceptive use, reliable interpretation of the results is significantly limited due to the small sample size and concerns over unmeasured and uncontrolled confounding, as well as questions about the suitability of the comparator selection and the validity of the venous thromboembolism definition.

A two-to-four fold increase in relative risk of postoperative thromboembolic complications has been reported with the use of oral contraceptives. The relative risk of venous thrombosis in women who have predisposing conditions is twice that of women without such medical conditions. If feasible, oral contraceptives should be discontinued at least four weeks prior to and for two weeks after elective surgery of a type associated with an increase in risk of thromboembolism and during and following prolonged immobilization. Since the immediate post-partum period is also associated with an increased risk of thromboembolism, oral contraceptives should be started no earlier than four weeks after delivery in women who elect not to breastfeed, or after a midtrimester pregnancy termination.

c. Cerebrovascular Diseases

Oral contraceptives have been shown to increase both the relative and attributable risks of cerebrovascular events (thrombotic and hemorrhagic strokes), although, in general, the risk is greatest among older (>35 years), hypertensive women who also smoke. Hypertension was found to be a risk factor for both users and nonusers, for both types of strokes, while smoking interacted to increase the risk for hemorrhagic strokes. Transient ischemic attacks have also been associated with oral contraceptive use.

In a large study, the relative risk of thrombotic strokes has been shown to range from 3 for normotensive users to 14 for users with severe hypertension. The relative risk of hemorrhagic stroke is reported to be 1.2 for nonsmokers who used oral contraceptives, 2.6 for smokers who did not use oral contraceptives, 7.6 for smokers who used oral contraceptives, 1.8 for normotensive users and 25.7 for users with severe hypertension. The attributable risk is also greater in older women. Oral contraceptives also increase the risk for stroke in women with other underlying risk factors such as certain inherited or acquired thrombophilias. Women with migraine (particularly migraine/headaches with focal neurological symptoms such as aura) who take combination oral contraceptives may be at an increased risk of stroke. (See CONTRAINDICATIONS.)

d. Dose-Related Risk of Vascular Disease From Oral Contraceptives

A positive association has been observed between the amount of estrogen and progestogen in oral contraceptives and the risk of vascular disease. A decline in serum high-density lipoproteins (HDL) has been reported with many progestational agents. A decline in serum high-density lipoproteins has been associated with an increased incidence of ischemic heart disease. Because estrogens increase HDL cholesterol, the net effect of an oral contraceptive depends on a balance achieved between doses of estrogen and progestogen and the nature and absolute amount of progestogen used in the contraceptive. The amount of both hormones should be considered in the choice of an oral contraceptive.

Minimizing exposure to estrogen and progestogen is in keeping with good principles of therapeutics. For any particular estrogen/progestogen combination, the dosage regimen prescribed should be one which contains the least amount of estrogen and progestogen that is compatible with a low failure rate and the needs of the individual patient. New acceptors of oral contraceptive agents should be started on preparations containing the lowest estrogen content which is judged appropriate for the individual patient.

e. Persistence of Risk of Vascular Disease

There are two studies which have shown persistence of risk of vascular disease for ever-users of oral contraceptives. In a study in the United States, the risk of developing myocardial infarction after discontinuing oral contraceptives persisted for at least 9 years for women 40 to 49 years who had used oral contraceptives for five or more years, but this increased risk was not demonstrated in other age groups.

In another study in Great Britain, the risk of developing cerebrovascular disease persisted for at least 6 years after discontinuation of oral contraceptives, although excess risk was very small. However, both studies were performed with oral contraceptive formulations containing 0.05 mg or higher of estrogens.

2. Estimates of Mortality From Contraceptive Use

One study gathered data from a variety of sources which have estimated the mortality rate associated with different methods of contraception at different ages (Table 3). These estimates include the combined risk of death associated with contraceptive methods plus the risk attributable to pregnancy in the event of method failure. Each method of contraception has its specific benefits and risks. The study concluded that with the exception of oral contraceptive users 35 and older who smoke and 40 and older who do not smoke, mortality associated with all methods of birth control is less than that associated with childbirth. The observation of a possible increase in risk of mortality with age for oral contraceptive users is based on data gathered in the 1970's — but not reported until 1983. However, current clinical practice involves the use of lower estrogen dose formulations combined with careful restriction of oral contraceptive use to women who do not have the various risk factors listed in this labeling.

Because of these changes in practice, and also because of some limited new data which suggest that the risk of cardiovascular disease with the use of oral contraceptives may now be less than previously observed, the Fertility and Maternal Health Drugs Advisory Committee was asked to review the topic in 1989. The Committee concluded that although cardiovascular disease risks may be increased with oral contraceptive use after age 40 in healthy nonsmoking women (even with the newer low-dose formulations), there are greater potential health risks associated with pregnancy in older women and with the alternative surgical and medical procedures which may be necessary if such women do not have access to effective and acceptable means of contraception.

Therefore, the Committee recommended that the benefits of oral contraceptive use by healthy nonsmoking women over 40 may outweigh the possible risks. Of course, older women, as all women who take oral contraceptives, should take the lowest possible dose formulation that is effective.

Table 3: Annual Number of Birth-Related or Method-Related Deaths Associated with Control of Fertility per 100,000 Nonsterile Women, by Fertility-Control Method and According to Age
Method of control and outcome | 15 to 19 | 20 to 24 | 25 to 29 | 30 to 34 | 35 to 39 | 40 to 44
No fertility-control methods* | 7 | 7.4 | 9.1 | 14.8 | 25.7 | 28.2
Oral contraceptives
nonsmoker** | 0.3 | 0.5 | 0.9 | 1.9 | 13.8 | 31.6
Oral contraceptives
smoker** | 2.2 | 3.4 | 6.6 | 13.5 | 51.1 | 117.2
IUD** | 0.8 | 0.8 | 1 | 1 | 1.4 | 1.4
Condom* | 1.1 | 1.6 | 0.7 | 0.2 | 0.3 | 0.4
Diaphragm/spermicide* | 1.9 | 1.2 | 1.2 | 1.3 | 2.2 | 2.8
Periodic abstinence* | 2.5 | 1.6 | 1.6 | 1.7 | 2.9 | 3.6
* Deaths are birth-related
**Deaths are method-related
Adapted from H.W. Ory, Family Planning Perspectives, 15:57-63, 1983.

3. Malignant Neoplasms

a. Breast Cancer

Levonorgestrel and ethinyl estradiol is contraindicated in females who currently have or have had breast cancer because breast cancer may be hormonally sensitive [see Contraindications].

Epidemiology studies have not found a consistent association between use of combined oral contraceptives (COCs) and breast cancer risk. Studies do not show an association between ever (current or past) use of COCs and risk of breast cancer. However, some studies report a small increase in the risk of breast cancer among current or recent users (<6 months since last use) and current users with longer duration of COC use [see Postmarketing Experience].

b. Cervical Cancer

Some studies suggest that oral contraceptive use has been associated with an increase in the risk of cervical intraepithelial neoplasia or invasive cervical cancer in some populations of women. However, there continues to be controversy about the extent to which such findings may be due to differences in sexual behavior and other factors.

In spite of many studies of the relationship between combination oral contraceptive use and breast and cervical cancers, a cause-and-effect relationship has not been established.

Endometrial biopsies performed in a subset of subjects (Study 1; n = 93) ages 18 to 49 years, after 6 to 12 months of use of levonorgestrel and ethinyl estradiol, did not reveal any hyperplasias or malignancies. Endometrial malignancy is rare in this age group, so change in the risk is unlikely to be detected with a study of this size.

4. Hepatic Neoplasia

Benign hepatic adenomas are associated with oral contraceptive use, although the incidence of these benign tumors is rare in the United States. Indirect calculations have estimated the attributable risk to be in the range of 3.3 cases/100,000 for users, a risk that increases after four or more years of use. Rupture of rare, benign, hepatic adenomas may cause death through intra-abdominal hemorrhage.

Studies from Britain have shown an increased risk of developing hepatocellular carcinoma in long-term (>8 years) oral contraceptive user. However, these cancers are extremely rare in the U.S. and the attributable risk (the excess incidence) of liver cancers in oral contraceptive users approaches less than one per million users.

RISK OF LIVER ENZYME ELEVATIONS WITH CONCOMITANT HEPATITIS C TREATMENT

During clinical trials with the Hepatitis C combination drug regimen that contains ombitasvir/paritaprevir/ritonavir, with or without dasabuvir, ALT elevations greater than 5 times the upper limit of normal (ULN), including some cases greater than 20 times the ULN, were significantly more frequent in women using ethinyl estradiol-containing medications such as COCs. Discontinue levonorgestrel and ethinyl estradiol prior to starting therapy with the combination drug regimen ombitasvir/paritaprevir/ritonavir, with or without dasabuvir [see Contraindications (4)]. Levonorgestrel and ethinyl estradiol can be restarted approximately 2 weeks following completion of treatment with the combination drug regimen.

5. Ocular Lesions

There have been clinical case reports of retinal thrombosis associated with the use of oral contraceptives that may lead to partial or complete loss of vision. Oral contraceptives should be discontinued if there is unexplained partial or complete loss of vision; onset of proptosis or diplopia; papilledema; or retinal vascular lesions. Appropriate diagnostic and therapeutic measures should be undertaken immediately.

6. Oral Contraceptive Use Before or During Early Pregnancy

Extensive epidemiological studies have revealed no increased risk of birth defects in infants born to women who have used oral contraceptives prior to pregnancy. Studies also do not suggest a teratogenic effect, particularly insofar as cardiac anomalies and limb-reduction defects are concerned, when taken inadvertently during early pregnancy (see CONTRAINDICATIONS section).

The administration of oral contraceptives to induce withdrawal bleeding should not be used as a test for pregnancy. Oral contraceptives should not be used during pregnancy to treat threatened or habitual abortion.

The possibility of pregnancy should be considered in any patient who may be experiencing symptoms of pregnancy, especially if she has not adhered to the prescribed schedule. Oral-contraceptive use must be discontinued if pregnancy is confirmed.

7. Gallbladder Disease

Combination oral contraceptives may worsen existing gallbladder disease and may accelerate the development of this disease in previously asymptomatic women. Earlier studies have reported an increased lifetime relative risk of gallbladder surgery in users of oral contraceptives and estrogens. More recent studies, however, have shown that the relative risk of developing gallbladder disease among oral contraceptive users may be minimal. The recent findings of minimal risk may be related to the use of oral contraceptive formulations containing lower hormonal doses of estrogens and progestogens.

8. Carbohydrate and Lipid Metabolic Effects

Oral contraceptives have been shown to cause glucose intolerance in a significant percentage of users. Oral contraceptives containing greater than 0.075 mg of estrogens cause hyperinsulinism, while lower doses of estrogen cause less glucose intolerance. Progestogens increase insulin secretion and create insulin resistance, this effect varying with different progestational agents. However, in the nondiabetic woman, oral contraceptives appear to have no effect on fasting blood glucose. Because of these demonstrated effects, prediabetic and diabetic women should be carefully observed while taking oral contraceptives.

A small proportion of women will have persistent hypertriglyceridemia while on the pill. As discussed earlier (see WARNINGS, 1a. and 1d.; PRECAUTIONS, 3.), changes in serum triglycerides and lipoprotein levels have been reported in oral contraceptive users.

9. Elevated Blood Pressure

An increase in blood pressure has been reported in women taking oral contraceptives and this increase is more likely in older oral contraceptive users and with continued use. Data from the Royal College of General Practitioners and subsequent randomized trials have shown that the incidence of hypertension increases with increasing quantities of progestogens.

Women with a history of hypertension or hypertension-related diseases, or renal disease should be encouraged to use another method of contraception. If women with hypertension elect to use oral contraceptives, they should be monitored closely and if significant elevation of blood pressure occurs, oral contraceptives should be discontinued (see CONTRAINDICATIONS section). For most women, elevated blood pressure will return to normal after stopping oral contraceptives, and there is no difference in the occurrence of hypertension among ever- and never-users.

10. Headache

The onset or exacerbation of migraine or development of headache with a new pattern that is recurrent, persistent, or severe requires discontinuation of oral contraceptives and evaluation of the cause. (See WARNINGS, 1c. and CONTRAINDICATIONS.)

11. Bleeding Irregularities

When prescribing levonorgestrel and ethinyl estradiol, the convenience of having no scheduled menstrual bleeding should be weighed against the inconvenience of unscheduled breakthrough bleeding and spotting. In Study 313-NA, 385/2,134 (18%) of women discontinued prematurely due to bleeding that was reported either as an adverse event or where bleeding was given as one of the reasons for discontinuation (see INDICATIONS AND USAGE, Clinical Studies).

Figure 4 shows the percentage of levonorgestrel and ethinyl estradiol subjects in study 313-NA by pill pack who experienced unscheduled bleeding or spotting only (Defined as “No sanitary protection required”).

Figure 4: Percentage of Subjects Reporting Bleeding or Spotting Only per Pill Pack

Figure 5 shows the percentage of levonorgestrel and ethinyl estradiol subjects with complete bleeding data in Study 313–NA who had 4 or more and 7 or more days of bleeding and/or spotting during each pill pack cycle. During pill pack 2, 67% of subjects experienced 4 or more days of bleeding and/or spotting and 54% of these subjects experienced 7 or more days of bleeding and/or spotting. During the final cycle of use of levonorgestrel and ethinyl estradiol (pill pack 13), these percentages were 31% and 20%, respectively.

Figure 5: Percentage of Subjects Reporting Greater Than or Equal to 4 or 7 Days of Bleeding and/or Spotting per Pill Pack (Study 313-NA)

As in any case of bleeding irregularities, nonhormonal causes should be considered and adequate diagnostic measures may be indicated to rule out pregnancy, infection, malignancy, or other conditions.

Some women may encounter post-pill amenorrhea or oligomenorrhea (possibly with anovulation), especially when such a condition was preexistent.

12. Ectopic Pregnancy

Ectopic as well as intrauterine pregnancy may occur in contraceptive failures.

PRECAUTIONS

1. General

Patients should be counseled that oral contraceptives do not protect against transmission of HIV (AIDS) and other sexually transmitted diseases (STDs) such as chlamydia, genital herpes, genital warts, gonorrhea, hepatitis B, and syphilis.

Scheduled withdrawal bleeding does not occur with the use of levonorgestrel and ethinyl estradiol, therefore, the absence of withdrawal bleeding cannot be used as a sign of an unexpected pregnancy and as such, unexpected pregnancy may be difficult to recognize. Although pregnancy is unlikely if levonorgestrel and ethinyl estradiol is taken as directed, if for any reason, pregnancy is suspected in a woman using levonorgestrel and ethinyl estradiol, a pregnancy test should be performed.

2. Physical Examination and Follow-Up

A periodic personal and family medical history and complete physical examination are appropriate for all women, including women using oral contraceptives. The physical examination, however, may be deferred until after initiation of oral contraceptives if requested by the woman and judged appropriate by the clinician. The physical examination should include special reference to blood pressure, breasts, abdomen, and pelvic organs, including cervical cytology, and relevant laboratory tests. In case of undiagnosed, persistent, or recurrent abnormal vaginal bleeding, appropriate diagnostic measures should be conducted to rule out malignancy. Women with a strong family history of breast cancer or who have breast nodules should be monitored with particular care.

3. Lipid Disorders

Women who are being treated for hyperlipidemias should be followed closely if they elect to use oral contraceptives. Some progestogens may elevate LDL levels and may render the control of hyperlipidemias more difficult. (See WARNINGS, 1a., 1d., and 8.)

A small proportion of women will have adverse lipid changes while taking oral contraceptives. Nonhormonal contraception should be considered in women with uncontrolled dyslipidemias. Persistent hypertriglyceridemia may occur in a small population of combination oral contraceptive users. Elevations of plasma triglycerides may lead to pancreatitis and other complications.

4. Liver Function

If jaundice develops in any woman receiving such drugs, the medication should be discontinued. Steroid hormones may be poorly metabolized in patients with impaired liver function.

5. Fluid Retention

Oral contraceptives may cause some degree of fluid retention. They should be prescribed with caution, and only with careful monitoring, in patients with conditions which might be aggravated by fluid retention.

6. Emotional Disorders

Patients becoming significantly depressed while taking oral contraceptives should stop the medication and use an alternate method of contraception in an attempt to determine whether the symptom is drug related. Women with a history of depression should be carefully observed and the drug discontinued if depression recurs to a serious degree.

7. Contact Lenses

Contact-lens wearers who develop visual changes or changes in lens tolerance should be assessed by an ophthalmologist.

8. Gastrointestinal

Diarrhea and/or vomiting may reduce hormone absorption resulting in decreased serum concentrations.

9. Drug Interactions

Changes in Contraceptive Effectiveness Associated with Coadministration of Other Products:

Contraceptive effectiveness may be reduced when hormonal contraceptives are coadministered with antibiotics, anticonvulsants, and other drugs that increase the metabolism of contraceptive steroids. This could result in unintended pregnancy or unscheduled bleeding. Examples include rifampin, rifabutin, barbiturates, primidone, phenylbutazone, phenytoin, dexamethasone, carbamazepine, felbamate, oxcarbazepine, topiramate, griseofulvin, and modafinil. In such cases a nonhormonal back-up method of birth control should be considered.

Several cases of contraceptive failure and unscheduled bleeding have been reported in the literature with concomitant administration of antibiotics such as ampicillin and other penicillins, and tetracyclines. However, clinical pharmacology studies investigating drug interactions between combined oral contraceptives and these antibiotics have reported inconsistent results. Enterohepatic recirculation of estrogens may also be decreased by substances that reduce gut transit time.

Several of the anti-HIV protease inhibitors have been studied with coadministration of oral combination hormonal contraceptives; significant changes (increase and decrease) in the plasma levels of the estrogen and progestin have been noted in some cases. The safety and efficacy of oral contraceptive products may be affected with coadministration of anti-HIV protease inhibitors. Health care professionals should refer to the label of the individual anti-HIV protease inhibitors for further drug-drug interaction information.

Herbal products containing St. John's Wort (Hypericum perforatum) may induce hepatic enzymes (cytochrome P 450) and p-glycoprotein transporter and may reduce the effectiveness of contraceptive steroids. This may also result in unscheduled bleeding.

Increase in Plasma Levels Associated with Coadministered Drugs:

Coadministration of atorvastatin and certain oral contraceptives containing ethinyl estradiol increases AUC values for ethinyl estradiol by approximately 20%. Ascorbic acid and acetaminophen increase the bioavailability of ethinyl estradiol since these drugs act as competitive inhibitors for sulfation of ethinyl estradiol in the gastrointestinal wall, a known pathway of elimination for ethinyl estradiol. CYP 3A4 inhibitors such as indinavir, itraconazole, ketoconazole, fluconazole, and troleandomycin may increase plasma hormone levels. Troleandomycin may also increase the risk of intrahepatic cholestasis during coadministration with combination oral contraceptives.

Changes in Plasma Levels of Coadministered Drugs:

Combination hormonal contraceptives containing some synthetic estrogens (eg, ethinyl estradiol) may inhibit the metabolism of other compounds. Increased plasma concentrations of cyclosporine, prednisolone and other corticosteroids, and theophylline have been reported with concomitant administration of oral contraceptives. Decreased plasma concentrations of acetaminophen and lamotrigine, and increased clearance of temazepam, salicylic acid, morphine, and clofibric acid, due to induction of conjugation (particularly glucuronidation), have been noted when these drugs were administered with oral contraceptives.

The prescribing information of concomitant medications should be consulted to identify potential interactions.

Concomitant Use with HCV Combination Therapy - Liver Enzyme Elevation

Do not co-administer levonorgestrel and ethinyl estradiol with HCV drug combinations containing ombitasvir/paritaprevir/ritonavir, with or without dasabuvir, due to potential for ALT elevations (see Warnings, RISK OF LIVER ENZYME ELEVATIONS WITH CONCOMITANT HEPATITIS C TREATMENT).

10. Interactions with Laboratory Tests

Certain endocrine- and liver-function tests and blood components may be affected by oral contraceptives:

1. Increased prothrombin and factors VII, VIII, IX, and X; decreased antithrombin 3; increased norepinephrine-induced platelet aggregability.
2. Increased thyroid-binding globulin (TBG) leading to increased circulating total thyroid hormone, as measured by protein-bound iodine (PBI), T4 by column or by radioimmunoassay. Free T3 resin uptake is decreased, reflecting the elevated TBG; free T4 concentration is unaltered.
3. Other binding proteins may be elevated in serum ie, corticosteroid binding globulin (CBG), sex hormone-binding globulins (SHBG) leading to increased levels of total circulating corticosteroids and sex steroids, respectively. Free or biologically active hormone concentrations are unchanged.
4. Triglycerides may be increased and levels of various other lipids and lipoproteins may be affected.
5. Glucose tolerance may be decreased.
6. Serum folate levels may be depressed by oral contraceptive therapy. This may be of clinical significance if a woman becomes pregnant shortly after discontinuing oral contraceptives.

11. Carcinogenesis

See WARNINGSsection.

12. Pregnancy

See CONTRAINDICATIONSand WARNINGSsections.

13. Nursing Mothers

Small amounts of oral contraceptive steroids and/or metabolites have been identified in the milk of nursing mothers, and a few adverse effects on the child have been reported, including jaundice and breast enlargement. In addition, combination oral contraceptives given in the postpartum period may interfere with lactation by decreasing the quantity and quality of breast milk. If possible, the nursing mother should be advised not to use combination oral contraceptives, but to use other forms of contraception until she has completely weaned her child.

14. Pediatric Use

Safety and efficacy of levonorgestrel and ethinyl estradiol have been established in women of reproductive age. Safety and efficacy are expected to be the same for postpubertal adolescents under the age of 16 and for users 16 years and older. Use of this product before menarche is not indicated.

15. Geriatric Use

This product has not been studied in women over 65 years of age and is not indicated in this population.

16. Information for the Patient

See DETAILED PATIENT LABELING printed below.

ADVERSE REACTIONS

An increased risk of the following serious adverse reactions (see WARNINGS section for additional information) has been associated with the use of oral contraceptives:

Thromboembolic and thrombotic disorders and other vascular problems (including thrombophlebitis and venous thrombosis with or without pulmonary embolism, mesenteric thrombosis, arterial thromboembolism, myocardial infarction, cerebral hemorrhage, cerebral thrombosis, transient ischemic attack), carcinoma of the reproductive organs and breasts, hepatic neoplasia/liver disease (including hepatic adenomas or benign liver tumors), ocular lesions (including retinal vascular thrombosis), gallbladder disease, carbohydrate and lipid effects, elevated blood pressure, and headache including migraine.

The following adverse reactions have been reported in patients receiving oral contraceptives and are believed to be drug related (alphabetically listed):

Acne

Amenorrhea

Anaphylactic/anaphylactoid reactions, including urticaria, angioedema, and severe reactions with respiratory and circulatory symptoms

Breast changes: tenderness, pain, enlargement, secretion

Budd-Chiari syndrome

Cervical erosion and secretion, change in

Cholestatic jaundice

Chorea, exacerbation of

Colitis

Contact lenses, intolerance to

Corneal curvature (steepening), change in

Dizziness

Edema/fluid retention

Erythema multiforme

Erythema nodosum

Focal nodular hyperplasia

Gastrointestinal symptoms (such as abdominal pain, cramps, and bloating)

Hirsutism

Infertility after discontinuation of treatment, temporary

Lactation, diminution in, when given immediately postpartum

Libido, change in

Melasma/chloasma which may persist

Menstrual flow, change in

Mood changes, including depression

Nausea

Nervousness

Pancreatitis

Porphyria, exacerbation of

Rash (allergic)

Scalp hair, loss of

Serum folate levels, decrease in

Spotting

Systemic lupus erythematosus, exacerbation of

Unscheduled bleeding

Vaginitis, including candidiasis

Varicose veins, aggravation of

Vomiting

Weight or appetite (increase or decrease), change in

The following adverse reactions have been reported in users of oral contraceptives:

Cataracts

Cystitis-like syndrome

Dysmenorrhea

Hemolytic uremic syndrome

Hemorrhagic eruption

Optic neuritis, which may lead to partial or complete loss of vision

Premenstrual syndrome

Renal function, impaired

Post Marketing Experience

Five studies that compared breast cancer risk between ever-users (current or past use) of COCs and never-users of COCs reported no association between ever use of COCs and breast cancer risk, with effect estimates ranging from 0.90 to 1.12 (Figure 6).

Three studies compared breast cancer risk between current or recent COC users (<6 months since last use) and never users of COCs (Figure 6). One of these studies reported no association between breast cancer risk and COC use. The other two studies found an increased relative risk of 1.19 to 1.33 with current or recent use. Both of these studies found an increased risk of breast cancer with current use of longer duration, with relative risks ranging from 1.03 with less than one year of COC use to approximately 1.4 with more than 8 to 10 years of COC use.

RR = relative risk; OR = odds ratio; HR = hazard ratio. “ever COC” are females with current or past COC use; “never COC use” are females that never used COCs.

OVERDOSAGE

Symptoms of oral contraceptive overdosage in adults and children may include nausea, vomiting, breast tenderness, dizziness, abdominal pain, drowsiness/fatigue; withdrawal bleeding may occur in females. There is no specific antidote and further treatment of overdose, if necessary, is directed to the symptoms.

NONCONTRACEPTIVE HEALTH BENEFITS

The following noncontraceptive health benefits related to the use of oral contraceptives are supported by epidemiological studies which largely utilized oral contraceptive formulations containing doses exceeding 0.035 mg of ethinyl estradiol or 0.05 mg of mestranol.

Effects on menses:

May decrease blood loss and may decrease the incidence of iron-deficiency anemia

May decrease incidence of dysmenorrhea

Effects related to inhibition of ovulation:

May decrease incidence of functional ovarian cysts

May decrease incidence of ectopic pregnancies

Effects from long-term use:

May decrease incidence of fibroadenomas and fibrocystic disease of the breast

May decrease incidence of acute pelvic inflammatory disease

May decrease incidence of endometrial cancer

May decrease incidence of ovarian cancer

DOSAGE AND ADMINISTRATION

To achieve maximum contraceptive effectiveness, levonorgestrel and ethinyl estradiol tablets must be taken exactly as directed and at intervals not exceeding 24 hours. The possibility of ovulation and conception prior to initiation of medication should be considered. Women who do not wish to become pregnant after discontinuation should be advised to immediately use another method of birth control. The dosage of levonorgestrel and ethinyl estradiol tablets is one brownish peach to light brown tablet daily without any tablet-free interval.

It is recommended that levonorgestrel and ethinyl estradiol tablets be taken at the same time each day.

Initiation of Therapy

Instructions for beginning levonorgestrel and ethinyl estradiol are provided in Table 4 below.

Table 4
Current contraceptive therapy | Levonorgestrel and ethinyl estradiol start day | Nonhormonal back-up method of birth control needed when correctly starting levonorgestrel and ethinyl estradiol?
None | Day 1 of patient's menstrual cycle (during the first 24 hours of her period) | No
21-day COC regimen OR 28-day COC regimen | Day 1 of patient's withdrawal bleed, at the latest 7 days after her last active tablet | No
Progestin-only pill | Day after taking a progestin-only pill | Yes, for the first 7 days of levonorgestrel and ethinyl estradiol tablet taking
Implant | Day of implant removal | Yes, for the first 7 days of levonorgestrel and ethinyl estradiol tablet taking
Injection | Day the next injection is due | Yes, for the first 7 days of levonorgestrel and ethinyl estradiol tablet taking

If spotting or unscheduled bleeding occurs, the patient is instructed to continue on the same regimen. This type of bleeding is usually transient and without significance; however, if the bleeding is persistent or prolonged, the patient is advised to consult her health care professional. The possibility of ovulation increases with each successive day that scheduled brownish peach to light brown tablets are missed. If the patient has not adhered to the prescribed schedule (missed one or more tablets or started taking them on a day later than she should have), the probability of pregnancy should be considered. Hormonal contraception must be discontinued if pregnancy is confirmed.

The risk of pregnancy increases with each tablet missed. For additional patient instructions regarding missed tablets, see the WHAT TO DO IF YOU MISS PILLS section in the DETAILED PATIENT LABELING below.

Levonorgestrel and ethinyl estradiol may be initiated no earlier than day 28 postpartum in the nonlactating mother or after a second-trimester abortion due to the increased risk for thromboembolism (see CONTRAINDICATIONS, WARNINGS, and PRECAUTIONS concerning thromboembolic disease). The patient should be advised to use a nonhormonal back-up method for the first 7 days of tablet-taking. However, if intercourse has already occurred, pregnancy should be excluded before the start of combined oral contraceptive use or the patient must wait for her first menstrual period.

In the case of first-trimester abortion, if the patient starts levonorgestrel and ethinyl estradiol immediately, additional contraceptive measures are not needed.

HOW SUPPLIED

Levonorgestrel and ethinyl estradiol tablets, USP (0.09 mg levonorgestrel, USP and 0.02 mg ethinyl estradiol, USP) are brownish peach to light brown, round, biconvex, film-coated tablets debossed with ‘E8’ on one side and are available as follows:

1 carton (NDC 68462-637-29) containing 3 individual pouches (NDC 68462-637-84). Each pouch contains 1 blister (NDC 68462-637-84) of 28 active tablets.

Store at 20oC to 25oC (68°F to 77oF); excursions permitted to 15ºC to 30oC (59ºF to 86oF) [See USP controlled room temperature].

References available upon request.

Distributed by:

Glenmark Pharmaceuticals Inc., USA
Elmwood Park, NJ 07407

Questions? 1 (888)721-7115
www.glenmarkpharma-us.com

June 2025

Brief Summary Patient Package Insert

This product (like all oral contraceptives) is intended to prevent pregnancy. Oral contraceptives do not protect against transmission of HIV (AIDS) and other sexually transmitted diseases (STDs) such as chlamydia, genital herpes, genital warts, gonorrhea, hepatitis B, and syphilis.

Oral contraceptives, also known as “birth-control pills” or “the pill,” are taken to prevent pregnancy, and when taken correctly, have a failure rate of approximately 1-2% per year (1 to 2 pregnancies per 100 women per year of use) when used without missing any pills. The average failure rate of large numbers of pill users is approximately 5% per year (5 pregnancies per 100 women per year of use) when women who miss pills are included. However, forgetting to take pills considerably increases the chances of pregnancy.

Levonorgestrel and ethinyl estradiol is a birth-control pill that is taken every day. When you take levonorgestrel and ethinyl estradiol, the lining of your uterus does not undergo the changes needed for menstruation, and therefore you do not have regular menstrual periods. You are likely to have unscheduled or unplanned bleeding or spotting when you start to use levonorgestrel and ethinyl estradiol. The number of days each month with unscheduled bleeding and spotting usually decreases over time for the majority of women. When using levonorgestrel and ethinyl estradiol, the convenience of having no regular menstrual periods should be weighed against the inconvenience of unscheduled or unplanned breakthrough bleeding and spotting.

For the majority of women, oral contraceptives can be taken safely. However, there are some women who are at high risk of developing certain serious diseases that can be life-threatening or may cause temporary or permanent disability or death. The risks associated with taking oral contraceptives increase significantly if you:

- smoke
- have high blood pressure, diabetes, high cholesterol, or a tendency to form blood clots, or are obese
- have or have had clotting disorders, heart attack, stroke, angina pectoris, cancer of the breast or sex organs, jaundice, malignant or benign liver tumors, or major surgery with prolonged immobilization
- have headaches with neurological symptoms

You should not take the pill if you suspect you are pregnant or have unexplained vaginal bleeding.

Although cardiovascular disease risks may be increased with oral contraceptive use in healthy, non-smoking women over 40 (even with the newer low-dose formulations), there are also greater potential health risks associated with pregnancy in older women.

Cigarette smoking increases the risk of serious adverse effects on the heart and blood vessels from oral contraceptive use. This risk increases with age and with the amount of smoking (15 or more cigarettes per day has been associated with a significantly increased risk) and is quite marked in women over 35 years of age. Women who use oral contraceptives should not smoke.

Most side effects of the pill are not serious. The most common such effects are nausea, vomiting, unscheduled bleeding, weight gain, breast tenderness, and difficulty wearing contact lenses. These side effects, especially nausea and vomiting, may subside within the first three months of use.

The serious side effects of the pill occur very infrequently, especially if you are in good health and do not smoke. However, you should know that the following medical conditions have been associated with or made worse by the pill:

1. Blood clots in the legs (thrombophlebitis), lungs (pulmonary embolism), stoppage or rupture of a blood vessel in the brain (stroke), blockage of blood vessels in the heart (heart attack and angina pectoris) or other organs of the body. As mentioned above, smoking increases the risk of heart attacks and strokes and subsequent serious medical consequences. Women with migraine also may be at increased risk of stroke with pill use.
2. Liver tumors, which may rupture and cause severe bleeding. A possible, but not definite, association has been found with the pill and liver cancer. However, liver cancers are extremely rare. The chance of developing liver cancer from using the pill is thus even rarer.
3. High blood pressure, although blood pressure usually returns to normal when the pill is stopped.

The symptoms associated with these serious side effects are discussed in the detailed leaflet given to you with your supply of pills. Notify your health care provider if you notice any unusual physical disturbances while taking the pill. In addition, drugs such as rifampin, as well as some anticonvulsants and some antibiotics, herbal preparations containing St. John's Wort (Hypericum perforatum), and HIV/AIDS drugs may decrease oral contraceptive effectiveness.

There may be slight increases in the risk of breast cancer among current users of hormonal birth control pills with longer duration of use of 8 years or more.

Some studies have found an increase in the incidence of cancer of the cervix in women who use oral contraceptives. However, this finding may be related to factors other than the use of oral contraceptives.

Taking the pill provides some important noncontraceptive benefits. These include less painful menstruation, fewer pelvic infections, and fewer cancers of the ovary and the lining of the uterus.

Be sure to discuss any medical condition you may have with your health care provider. Your health care provider will take a medical and family history before prescribing oral contraceptives and will examine you. The physical examination may be delayed to another time if you request it, and the health care provider believes that it is appropriate to postpone it. You should be reexamined at least once a year while taking oral contraceptives. The detailed patient information leaflet gives you further information which you should read and discuss with your health care provider.

What You Should Know About Your Menstrual Cycle When You Use levonorgestrel and ethinyl estradiol

You are likely to have unscheduled or unplanned bleeding or spotting when you start to use levonorgestrel and ethinyl estradiol. The number of days each month with bleeding or spotting usually decreases over time in the majority of women. In a study of levonorgestrel and ethinyl estradiol, about 5 out of 10 women had 7 or more days of bleeding or spotting while using their third 28-day pill pack of levonorgestrel and ethinyl estradiol. The number of women with 7 or more days of bleeding or spotting decreased to 3 out of 10 women during the use of their seventh pill pack. Among women who continued to use levonorgestrel and ethinyl estradiol for one year, about 6 out of 10 women had no bleeding or spotting during their last month of use.

Do not stop taking levonorgestrel and ethinyl estradiol because of bleeding or spotting as this will increase your chance of getting pregnant. If the spotting or bleeding continues for more than 7 consecutive days or if the bleeding is heavy, call your health care provider.

Can I Get Pregnant While Taking levonorgestrel and ethinyl estradiol?

You are not likely to get pregnant if you take levonorgestrel and ethinyl estradiol at the same time everyday as directed by your health care provider. Because regular monthly bleeding does not occur on levonorgestrel and ethinyl estradiol, it may be difficult to recognize if you get pregnant. If you suspect that you may be pregnant, or if you have symptoms of pregnancy such as nausea/vomiting or unusual breast tenderness, you should have a pregnancy test and you should contact your health care professional. Stop taking levonorgestrel and ethinyl estradiol if you are pregnant.

Instructions for the Patient

HOW TO TAKE LEVONORGESTREL AND ETHINYL ESTRADIOL TABLETS

Important Points to Remember

Before You Start Taking levonorgestrel and ethinyl estradiol:

1. BE SURE TO READ THESE DIRECTIONS:
  Before you start taking levonorgestrel and ethinyl estradiol.
  And
  Anytime you are not sure what to do.
2. THE RIGHT WAY TO TAKE LEVONORGESTREL AND ETHINYL ESTRADIOL IS TO TAKE ONE PILL EVERY DAY AT THE SAME TIME.
  If you miss pills, you could get pregnant. This includes starting the pack late. The more pills you miss, the more likely you are to get pregnant. See “WHAT TO DO IF YOU MISS PILLS” below.
3. MANY WOMEN HAVE SPOTTING OR LIGHT BLEEDING, OR MAY FEEL SICK TO THEIR STOMACH DURING THE FIRST 1 to 3 PACKS OF PILLS.
  If you feel sick to your stomach, do not stop taking levonorgestrel and ethinyl estradiol. This will usually go away. If it doesn't go away, check with your health care professional.
4. MOST WOMEN HAVE SPOTTING OR BLEEDING DURING THE FIRST FEW MONTHS OF TAKING LEVONORGESTREL AND ETHINYL ESTRADIOL. Do not stop taking your pills even if you are having bleeding or spotting. If the bleeding or spotting lasts for more than 7 consecutive days, talk to your health care provider.
5. MISSING PILLS CAN ALSO CAUSE SPOTTING OR LIGHT BLEEDING, even when you make up these missed pills.
  On the days you take 2 pills to make up for missed pills, you could also feel a little sick to your stomach.
6. IF YOU VOMIT (within 4 hours after you take your pill), you should follow the instructions for WHAT TO DO IF YOU MISS PILLS. IF YOU HAVE DIARRHEA or IF YOU TAKE SOME MEDICINES, including some antibiotics, your pills may not work as well.
  Use a back-up nonhormonal method (such as condoms and/or spermicide) until you check with your health care professional.
7. IF YOU HAVE TROUBLE REMEMBERING TO TAKE LEVONORGESTREL AND ETHINYL ESTRADIOL, talk to your health care professional about how to make pill-taking easier or about using another method of birth control.
8. IF YOU HAVE ANY QUESTIONS OR ARE UNSURE ABOUT THE INFORMATION IN THIS LEAFLET, call your health care professional.

BEFORE YOU START TAKING LEVONORGESTREL AND ETHINYL ESTRADIOL

1. DECIDE WHAT TIME OF DAY YOU WANT TO TAKE YOUR PILL. It is important to take your pill at the SAME TIME every day.
2. LOOK AT YOUR LEVONORGESTREL AND ETHINYL ESTRADIOL BLISTER. The pill pack has 28 “active” brownish peach to light brown pills (with hormones).
3. Locate the top row of the blister.
4. Pick the day label strip that starts with the first day of your period (this is the day you start bleeding or spotting, even if it is almost midnight when the bleeding begins).
5. Place the day label strip on the tablet blister over the area that has the days of the week (starting with Sunday) imprinted in the plastic.

1. When it comes time to take levonorgestrel and ethinyl estradiol, you will take each pill until the blister is empty.
2. BE SURE YOU HAVE READY AT ALL TIMES:
  ANOTHER KIND OF NONHORMONAL BIRTH CONTROL (such as condoms and/or spermicide) to use as a back-up in case you miss pills.
  AN EXTRA, FULL PILL PACK.

WHEN TO START THE FIRST PACK OF LEVONORGESTREL AND ETHINYL ESTRADIOL

Day 1 Start

1. Take the first “active” brownish peach to light brown pill of the first pack during the first 24 hours of your period.
2. You will not need to use a back-up nonhormonal method of birth control, since you are starting the pill at the beginning of your period.

WHAT TO DO DURING THE MONTH

1. TAKE ONE PILL AT THE SAME TIME EVERY DAY UNTIL THE BLISTER PACK IS EMPTY. Do not skip pills even if you are spotting or bleeding or feel sick to your stomach (nausea).
  Do not skip pills even if you do not have sex very often.
2. WHEN YOU FINISH A PACK
  Start the next pack on the day after your last pill. Do not wait any days between packs.

IF YOU SWITCH FROM ANOTHER BRAND OF COMBINATION PILLS:

When switching from a 21 pill pack: Start levonorgestrel and ethinyl estradiol on the first day of your period (withdrawal bleed). Be sure that no more than 7 days pass between the last day of your 21-day pack and your first levonorgestrel and ethinyl estradiol pill.

When switching from a 28 pill pack (21 active and 7 inactive pills, or 24 active and 4 inactive pills): Start levonorgestrel and ethinyl estradiol on the first day of your period (withdrawal bleed). Be sure that no more than 7 days pass after the last active pill and your first levonorgestrel and ethinyl estradiol pill.

IF YOU SWITCH FROM ANOTHER TYPE OF BIRTH CONTROL

When switching from other types of birth control such as pills containing only a progestin (progestin only pill or POP), an injection, or an implant, your health care professional will provide you with instructions for when to start levonorgestrel and ethinyl estradiol.

WHAT TO DO IF YOU MISS PILLS

Combination oral contraceptives may not be as effective if you miss pills. Instructions for what to do if you miss pills are provided in the following table.

# of pills missed in a row | What to do when you miss a pill(s)
1 missed pill | • Take the missed pill as soon as you remember. THEN • Take the next pill at your regular time. This means you may take 2 pills in 1 day. • You COULD BECOME PREGNANT if you have sex during the 7 days after you restart your pills. You MUST use a nonhormonal birth-control method (such as condoms and/or spermicide) as a back-up for those 7 days.
2 missed pills and remembered on the day of the second missed pill | • Take 2 missed pills on the day you remember. The following day you are back on schedule to take 1 pill a day. For example, you take your pills in the morning and you missed 1 pill on Monday and 1 on Tuesday. On Tuesday evening you remembered that you missed your Monday and Tuesday pills. You take the 2 missed pills on Tuesday evening and on Wednesday morning you're back on schedule and you take 1 pill. • You COULD BECOME PREGNANT if you have sex during the 7 days after you restart your pills. You MUST use a nonhormonal birth-control method (such as condoms and/or spermicide) as a back-up for those 7 days.
2 missed pills and remembered on the day after the second pill is missed | • Take 2 missed pills on the day you remember. The next day you take 2 pills. The following day you are back on schedule to take your pills. For example, you take your pills in the morning and you missed 1 pill on Monday and 1 on Tuesday. On Wednesday morning you remembered that you missed your Monday and Tuesday pills. You take the 2 missed pills on Wednesday morning and 2 pills on Thursday morning. On Friday morning you're back on schedule and you take 1 pill. • You COULD BECOME PREGNANT if you have sex during the 7 days after you restart your pills. You MUST use a nonhormonal birth-control method (such as condoms and/or spermicide) as a back-up for those 7 days.
3 or more missed pills | • Contact your health care professional for further advice. Keep taking one pill every day until you reach your health care professional. Do not take the missed pills. • You COULD BECOME PREGNANT if you have sex during the 7 days after you restart your pills. You MUST use a nonhormonal birth-control method (such as condoms and/or spermicide) as a back-up for those 7 days.

FINALLY, IF YOU ARE STILL NOT SURE WHAT TO DO ABOUT THE PILLS YOU HAVE MISSED Use a BACK-UP NONHORMONAL BIRTH-CONTROL METHOD anytime you have sex.

PREGNANCY AFTER STOPPING THE PILL

If you do not desire pregnancy, you should use another method of birth-control immediately after stopping levonorgestrel and ethinyl estradiol. You can get pregnant within days after stopping levonorgestrel and ethinyl estradiol.

For additional information see “Detailed Patient Labeling.”

DETAILED PATIENT LABELING

This product (like all oral contraceptives) is intended to prevent pregnancy. Oral contraceptives do not protect against transmission of HIV (AIDS) and other sexually transmitted diseases (STDs) such as chlamydia, genital herpes, genital warts, gonorrhea, hepatitis B, and syphilis.

INTRODUCTION

Any woman who considers using oral contraceptives (the “birth-control pill” or “the pill”) should understand the benefits and risks of using this form of birth control. This leaflet will give you much of the information you will need to make this decision and will also help you determine if you are at risk of developing any of the serious side effects of the pill. It will tell you how to use the pill properly so that it will be as effective as possible. However, this leaflet is not a replacement for a careful discussion between you and your health care professional. You should discuss the information provided in this leaflet with him or her, both when you first start taking the pill and during your revisits. You should also follow your health care professional’s advice with regard to regular check-ups while you are on the pill.

Levonorgestrel and ethinyl estradiol is a birth-control pill that is taken every day. When you take levonorgestrel and ethinyl estradiol, the lining of your uterus does not undergo the changes needed for menstruation, and therefore you do not have regular menstrual periods. You are likely to have unscheduled or unplanned bleeding or spotting when you start to use levonorgestrel and ethinyl estradiol. The number of days each month with unscheduled bleeding and spotting usually decreases over time for the majority of women. When using levonorgestrel and ethinyl estradiol, the convenience of having no regular menstrual periods should be weighed against the inconvenience of unscheduled or unplanned breakthrough bleeding and spotting.

EFFECTIVENESS OF ORAL CONTRACEPTIVES

Oral contraceptives or “birth-control pills” or “the pill” are used to prevent pregnancy and are more effective than other nonsurgical methods of birth control. When they are taken correctly, without missing any pills the chance of becoming pregnant is approximately 1-2% per year (1 to 2 pregnancies per 100 women per year of use). Average failure rates are approximately 5% per year (5 pregnancies per 100 women per year of use) when women who miss pills are included. The chance of becoming pregnant increases with each missed pill.

In comparison, average failure rates for other methods of birth control during the first year of use are as follows:

IUD: 0.1-2% | Female condom alone: 21%
Depo-Provera® (injectable progestogen): 0.3% | Cervical cap
Norplant® System (levonorgestrel implants): 0.05% | Never given birth: 20%
Diaphragm with spermicides: 20% | Given birth: 40%
Spermicides alone: 26% | Periodic abstinence: 25%
Male condom alone: 14% | No methods: 85%

WHO SHOULD NOT TAKE ORAL CONTRACEPTIVES

Although cardiovascular disease risks may be increased with oral contraceptive use in healthy, non-smoking women over 40 (even with the newer low-dose formulations), there are also greater potential health risks associated with pregnancy in older women.

BOXED WARNING

Cigarette smoking increases the risk of serious adverse effects on the heart and blood vessels from oral contraceptive use. This risk increases with age and with the amount of smoking (15 or more cigarettes per day has been associated with a significantly increased risk) and is quite marked in women over 35 years of age. Women who use oral contraceptives should not smoke.

Some women should not use the pill. For example, you should not take the pill if you have any of the following conditions:

1. History of heart attack or stroke.
2. Blood clots in the legs (thrombophlebitis), lungs (pulmonary embolism), or eyes.
3. History of blood clots in the deep veins of your legs.
4. Hereditary or acquired blood clotting disorders
5. Chest pain (angina pectoris).
6. Known or suspected breast cancer or cancer of the lining of the uterus, cervix or vagina, or certain hormonally-sensitive cancers.
7. Unexplained vaginal bleeding (until a diagnosis is reached by your health care professional).
8. Liver tumor (benign or cancerous) or active liver disease.
9. Take any Hepatitis C drug combination containing ombitasvir/paritaprevir/ritonavir, with or without dasabuvir. This may increase levels of the liver enzyme "alanine aminotransferase" (ALT) in the blood.
10. Yellowing of the whites of the eyes or of the skin (jaundice) during pregnancy or during previous use of the pill.
11. Known or suspected pregnancy.
12. A need for surgery with prolonged bedrest.
13. Heart valve or heart rhythm disorders that may be associated with formation of blood clots.
14. Diabetes affecting your circulation.
15. Headaches with neurological symptoms such as aura.
16. Uncontrolled high blood pressure.
17. Allergy or hypersensitivity to any of the components of levonorgestrel and ethinyl estradiol tablets

Tell your health care professional if you have had any of these conditions. Your health care professional can recommend another method of birth control.

OTHER CONSIDERATIONS BEFORE TAKING ORAL CONTRACEPTIVES

Tell your health care professional if you or any family member has ever had:

1. Breast nodules, fibrocystic disease of the breast, an abnormal breast X-ray or mammogram.
2. Diabetes.
3. Elevated cholesterol or triglycerides.
4. High blood pressure.
5. A tendency to form blood clots.
6. Migraine or other headaches or epilepsy.
7. Depression.
8. Gallbladder, liver, heart, or kidney disease.
9. History of scanty or irregular menstrual periods.

Women with any of these conditions should be checked often by their health care professional if they choose to use oral contraceptives. Also, be sure to inform your health care professional if you smoke or are on any medications.

RISKS OF TAKING ORAL CONTRACEPTIVES

Levonorgestrel and ethinyl estradiol is a non-cyclic oral contraceptive that provides a low daily dose of estrogen and progestin; however, levonorgestrel and ethinyl estradiol provides women with more hormonal exposure on a yearly basis (13 additional weeks of hormone intake per year) than conventional cyclic oral contraceptives containing the same strength of synthetic estrogens and similar strength of progestins.

1. Risk of Developing Blood Clots

Blood clots and blockage of blood vessels are the most serious side effects of taking oral contraceptives and can cause death or serious disability. In particular, a clot in the legs can cause thrombophlebitis and a clot that travels to the lungs can cause a sudden blocking of the vessel carrying blood to the lungs. Rarely, clots occur in the blood vessels of the eye and may cause blindness, double vision, or impaired vision.

Users of combination oral contraceptives have a higher risk of developing blood clots compared to non-users. This risk is highest during the first year of combination oral contraceptive use.

If you take oral contraceptives and need elective surgery, need to stay in bed for a prolonged illness or injury, or have recently delivered a baby, you may be at risk of developing blood clots. You should consult your health care professional about stopping oral contraceptives three to four weeks before surgery and not taking oral contraceptives for two weeks after surgery or during bed rest. You should also not take oral contraceptives soon after delivery of a baby or after a midtrimester pregnancy termination. It is advisable to wait for at least four weeks after delivery if you are not breast-feeding. If you are breast-feeding, you should wait until you have weaned your child before using the pill. (See also the section While Breast-Feeding in GENERAL PRECAUTIONS.)

The risk of blood clots is greater in users of combination oral contraceptives compared to nonusers. This risk may be higher in users of high-dose pills (those containing 0.05 mg or more of estrogen) and may also be greater with longer use. In addition, some of these increased risks may continue for a number of years after stopping combination oral contraceptives. The risk of abnormal blood clotting increases with age in both users and nonusers of combination oral contraceptives, but the increased risk from the oral contraceptive appears to be present at all ages.

The excess risk of blood clots is highest during the first year a woman ever uses a combined oral contraceptive. This increased risk is lower than blood clots associated with pregnancy. The use of combination oral contraceptives also increases the risk of other clotting disorders, including heart attack and stroke. Blood clots in veins cause death in 1% to 2% of cases. The risk of clotting is further increased in women with other conditions. Examples include: smoking, high blood pressure, abnormal lipid levels, certain inherited or acquired clotting disorders, obesity, surgery or injury, recent delivery or second trimester abortion, prolonged inactivity or bedrest. If possible, combination oral contraceptives should be stopped before surgery and during prolonged inactivity or bedrest.

Cigarette smoking increases the risk of serious cardiovascular events. This risk increases with age and amount of smoking and is quite pronounced in women over 35. Women who use combination oral contraceptives should be strongly advised not to smoke. If you smoke you should talk to your health care professional before taking combination oral contraceptives.

2. Heart Attacks and Strokes

Oral contraceptives may increase the tendency to develop strokes or transient ischemic attacks (blockage or rupture of blood vessels in the brain), and angina pectoris and heart attacks (blockage of blood vessels in the heart). Any of these conditions can cause death or serious disability.

Smoking greatly increases the possibility of suffering heart attacks and strokes. Furthermore, smoking and the use of oral contraceptives greatly increase the chances of developing and dying of heart disease.

Women with migraine (especially migraine/headache with neurological symptoms such as aura) who take oral contraceptives also may be at higher risk of stroke and must not use combination oral contraceptives (see section WHO SHOULD NOT TAKE ORAL CONTRACEPTIVES).

3. Gallbladder Disease

Oral contraceptive users probably have a greater risk than nonusers of having gallbladder disease, although this risk may be related to pills containing high doses of estrogens. Oral contraceptives may worsen existing gallbladder disease or accelerate the development of gallbladder disease in women previously without symptoms.

4. Liver Tumor

In rare cases, oral contraceptives can cause benign but dangerous liver tumors. These benign liver tumors can rupture and cause fatal internal bleeding. In addition, a possible but not definite association has been found with the pill and liver cancers in two studies in which a few women who developed these very rare cancers were found to have used oral contraceptives for long periods. However, liver cancers are extremely rare. The chance of developing liver cancer from using the pill is thus even rarer.

5. Risk of Cancer

It is not known if hormonal birth control pills cause breast cancer. Some studies, but not all, suggest that there could be a slight increase in the risk of breast cancer among current users with longer duration of use.

If you have breast cancer now, or have had it in the past, do not use hormonal birth control because some breast cancers are sensitive to hormones.

Some studies have found an increase in the incidence of cancer of the cervix in women who use oral contraceptives. However, this finding may be related to factors other than the use of oral contraceptives.

6. Lipid Metabolism and Pancreatitis

There have been reports of increases of blood cholesterol and triglycerides in users of combination oral contraceptives. Increases in triglycerides have led to inflammation of the pancreas (pancreatitis) in some cases.

Estimated Risk of Death from a Birth-Control Method or Pregnancy

All methods of birth control and pregnancy are associated with a risk of developing certain diseases which may lead to disability or death. An estimate of the number of deaths associated with different methods of birth control and pregnancy has been calculated and is shown in the following table.

Annual Number of Birth-Related or Method-Related Deaths Associated with Control of Fertility per 100,000 Nonsterile Women, by Fertility-Control Method and According to Age
Method of control and outcome | 15-19 | 20-24 | 25-29 | 30-34 | 35-39 | 40-44
No fertility-control methods* | 7.0 | 7.4 | 9.1 | 14.8 | 25.7 | 28.2
Oral contraceptives
nonsmoker** | 0.3 | 0.5 | 0.9 | 1.9 | 13.8 | 31.6
Oral contraceptives
smoker** | 2.2 | 3.4 | 6.6 | 13.5 | 51.1 | 117.2
IUD** | 0.8 | 0.8 | 1.0 | 1.0 | 1.4 | 1.4
Condom* | 1.1 | 1.6 | 0.7 | 0.2 | 0.3 | 0.4
Diaphragm/spermicide* | 1.9 | 1.2 | 1.2 | 1.3 | 2.2 | 2.8
Periodic abstinence* | 2.5 | 1.6 | 1.6 | 1.7 | 2.9 | 3.6
* Deaths are birth-related; **Deaths are method-related

In the above table, the risk of death from any birth-control method is less than the risk of childbirth, except for oral contraceptive users over the age of 35 who smoke and pill users over the age of 40 even if they do not smoke. It can be seen in the table that for women aged 15 to 39, the risk of death was highest with pregnancy (7 to 26 deaths per 100,000 women, depending on age). Among pill users who do not smoke, the risk of death was always lower than that associated with pregnancy for any age group, except for those women over the age of 40, when the risk increases to 32 deaths per 100,000 women, compared to 28 associated with pregnancy at that age. However, for pill users who smoke and are over the age of 35, the estimated number of deaths exceeds those for other methods of birth control. If a woman is over the age of 40 and smokes, her estimated risk of death is four times higher (117/100,000 women) than the estimated risk associated with pregnancy (28/100,000 women) in that age group.

The suggestion that women over 40 who do not smoke should not take oral contraceptives is based on information from older high-dose pills. An Advisory Committee of the FDA discussed this issue in 1989 and recommended that the benefits of oral contraceptive use by healthy, nonsmoking women over 40 years of age may outweigh the possible risks. Older women, as all women, who take oral contraceptives, should take an oral contraceptive which contains the least amount of estrogen and progestogen that is compatible with the individual patient needs.

WARNING SIGNALS

If any of these adverse effects occur while you are taking oral contraceptives, call your health care professional immediately:

1. Sharp chest pain, coughing of blood, or sudden shortness of breath (indicating a possible clot in the lung).
2. Pain in the calf (indicating a possible clot in the leg).
3. Crushing chest pain or heaviness in the chest (indicating a possible heart attack).
4. Sudden severe headache or vomiting, dizziness or fainting, disturbances of vision or speech, weakness, or numbness in an arm or leg (indicating a possible stroke).
5. Sudden partial or complete loss of vision (indicating a possible clot in the eye).
6. Breast lumps (indicating possible breast cancer or fibrocystic disease of the breast; ask your health care professional to show you how to examine your breasts).
7. Severe pain or tenderness in the stomach area (indicating a possibly ruptured liver tumor).
8. Difficulty in sleeping, weakness, lack of energy, fatigue, or change in mood (possibly indicating severe depression).
9. Jaundice or a yellowing of the skin or eyeballs, accompanied frequently by fever, fatigue, loss of appetite, dark-colored urine, or light-colored bowel movements (indicating possible liver problems).

SIDE EFFECTS OF ORAL CONTRACEPTIVES

1. Unscheduled Bleeding and Spotting

Unscheduled bleeding or spotting is likely to occur while you are taking levonorgestrel and ethinyl estradiol. Unscheduled bleeding or spotting occurs most often during the first seven pill packs of levonorgestrel and ethinyl estradiol use. It tends to decrease with subsequent pill packs of use, but may occur after you have been taking levonorgestrel and ethinyl estradiol for some time. In a study of levonorgestrel and ethinyl estradiol, 60% of women had bleeding and/or spotting during the sixth pill pack of use. Bleeding and/or spotting decreased to 48% during pill pack 9, and to 41% during pill pack 13. In this study, the percentage of women who discontinued treatment, at least in part, due to unscheduled bleeding or spotting was 18%.

The following figure shows by pill pack, the percentage of women using levonorgestrel and ethinyl estradiol in a North American study, who experienced unscheduled bleeding or spotting only.

Percentage of Subjects Reporting Bleeding or Spotting Only per Pill Pack

The following figure shows the percentage of women using levonorgestrel and ethinyl estradiol in a North American study who had 4 or more and 7 or more days of bleeding and/or spotting during each pill pack. During pill pack 2, 67% of women experienced 4 or more days of bleeding and/or spotting and 54% of these women experienced 7 or more days of bleeding and/or spotting. During the final pill pack of use of levonorgestrel and ethinyl estradiol (pill pack 13), these percentages were 31% and 20%, respectively.

Percentage of Subjects Reporting Greater Than or Equal to 4 or 7 Days of Bleeding and/or Spotting per Pill Pack (Study 313-NA)

It is important to continue taking your pills at the same time each day according to your daily routine, even if you are having unscheduled bleeding or spotting. If the unscheduled bleeding and/or spotting continue for an extended period of time (for example, 7 consecutive days) or if the bleeding is heavy, contact your health care professional.

2. Contact Lenses

If you wear contact lenses and notice a change in vision or an inability to wear your lenses, contact your health care professional.

3. Fluid Retention

Oral contraceptives may cause edema (fluid retention) with swelling of the fingers or ankles and may raise your blood pressure. If you experience fluid retention, contact your health care professional.

4. Melasma

A spotty darkening of the skin is possible, particularly of the face.

5. Other Side Effects

Other side effects may include nausea, breast tenderness, change in appetite, headache, nervousness, depression, dizziness, loss of scalp hair, rash, vaginal infections, inflammation of the pancreas, and allergic reactions.

If these or any other side effects bother you, contact your health care professional.

GENERAL PRECAUTIONS

1. Use of Oral Contraceptives Before or During Early Pregnancy

Because regular monthly bleeding does not occur on levonorgestrel and ethinyl estradiol, an unexpected pregnancy may be difficult to recognize. If you suspect you may be pregnant, or if you have symptoms of pregnancy such as nausea/vomiting or unusual breast tenderness, a pregnancy test should be performed and you should contact your health care professional. Stop taking levonorgestrel and ethinyl estradiol if you are pregnant. Pregnancy is unlikely if the pill is taken as directed.

There is no conclusive evidence that oral contraceptive use is associated with an increase in birth defects, when taken inadvertently during early pregnancy. Previously, a few studies had reported that oral contraceptives might be associated with birth defects, but these studies have not been confirmed. Nevertheless, oral contraceptives should not be used during pregnancy. You should check with your health care professional about risks to your unborn child of any medication taken during pregnancy.

2. While Breastfeeding

If you are breastfeeding, consult your health care professional before starting oral contraceptives. Some of the drug will be passed on to the child in the milk. A few adverse effects on the child have been reported, including yellowing of the skin (jaundice) and breast enlargement. In addition, oral contraceptives may decrease the amount and quality of your milk. If possible, do not use oral contraceptives while breastfeeding. You should use another method of contraception since breastfeeding provides only partial protection from becoming pregnant and this partial protection decreases significantly as you breastfeed for longer periods of time. You should consider starting oral contraceptives only after you have weaned your child completely.

3. Laboratory Tests

If you are scheduled for any laboratory tests, tell your health care professional you are taking birth-control pills. Certain blood tests may be affected by birth-control pills.

4. Drug Interactions

Certain drugs may interact with birth-control pills to make them less effective in preventing pregnancy or cause an increase in unscheduled bleeding. Such drugs include rifampin, drugs used for epilepsy such as barbiturates (for example, phenobarbital) and phenytoin (Dilantin® is one brand of this drug), primidone (Mysoline®), topiramate (Topamax®), carbamazepine (Tegretol® is one brand of this drug), phenylbutazone (Butazolidin® is one brand), some drugs used for HIV or AIDS such as ritonavir (Norvir®), modafinil (Provigil®) and possibly certain antibiotics (such as ampicillin and other penicillins, and tetracyclines), and herbal products containing St. John's Wort (Hypericum perforatum). You may also need to use a nonhormonal method of contraception during any pill pack in which you take drugs that can make oral contraceptives less effective.

You may be at higher risk for a specific type of liver dysfunction if you take troleandomycin and oral contraceptives at the same time.

You should inform your health care professional about all medicines you are taking, including nonprescription products.

5. Sexually Transmitted Diseases

This product (like all oral contraceptives) is intended to prevent pregnancy. It does not protect against transmission of HIV (AIDS) and other sexually transmitted diseases such as chlamydia, genital herpes, genital warts, gonorrhea, hepatitis B, and syphilis.

What You Should Know About Your Menstrual Cycle When You Use levonorgestrel and ethinyl estradiol

You are likely to have unscheduled or unplanned bleeding or spotting when you start to use levonorgestrel and ethinyl estradiol. The number of days each month with bleeding or spotting usually decreases over time in the majority of women. In a study of levonorgestrel and ethinyl estradiol, about 5 out of 10 women had 7 or more days of bleeding or spotting while using their third 28-day pill pack of levonorgestrel and ethinyl estradiol. The number of women with 7 or more days of bleeding or spotting decreased to 3 out of 10 women during the use of their seventh pill pack. Among women who continued to use levonorgestrel and ethinyl estradiol for one year, about 6 out of 10 women had no bleeding or spotting during their last month of use.

Do not stop taking levonorgestrel and ethinyl estradiol because of bleeding or spotting as this will increase your chance of getting pregnant. If the spotting or bleeding continues for more than 7 consecutive days or if the bleeding is heavy, call your health care provider.

Can I Get Pregnant While Taking levonorgestrel and ethinyl estradiol?

You are not likely to get pregnant if you take levonorgestrel and ethinyl estradiol at the same time everyday as directed by your health care provider. Because regular monthly bleeding does not occur on levonorgestrel and ethinyl estradiol, it may be difficult to recognize if you get pregnant. If you suspect that you may be pregnant, or if you have symptoms of pregnancy such as nausea/vomiting or unusual breast tenderness, you should have a pregnancy test and you should contact your health care professional. Stop taking levonorgestrel and ethinyl estradiol if you are pregnant.

HOW TO TAKE LEVONORGESTREL AND ETHINYL ESTRADIOL TABLETS USP

Important Points to Remember

Before You Start Taking levonorgestrel and ethinyl estradiol:

1. BE SURE TO READ THESE DIRECTIONS:
  Before you start taking levonorgestrel and ethinyl estradiol.
  And
  Anytime you are not sure what to do.
2. THE RIGHT WAY TO TAKE LEVONORGESTREL AND ETHINYL ESTRADIOL IS TO TAKE ONE PILL EVERY DAY AT THE SAME TIME.
  If you miss pills, you could get pregnant. This includes starting the pack late. The more pills you miss, the more likely you are to get pregnant. See “WHAT TO DO IF YOU MISS PILLS” below.
3. MANY WOMEN HAVE SPOTTING OR LIGHT BLEEDING, OR MAY FEEL SICK TO THEIR STOMACH DURING THE FIRST 1-3 PACKS OF PILLS.
  If you feel sick to your stomach, do not stop taking levonorgestrel and ethinyl estradiol. This will usually go away. If it doesn't go away, check with your health care professional.
4. MOST WOMEN HAVE SPOTTING OR BLEEDING DURING THE FIRST FEW MONTHS OF TAKING LEVONORGESTREL AND ETHINYL ESTRADIOL. Do not stop taking your pills even if you are having bleeding or spotting. If the bleeding or spotting lasts for more than 7 consecutive days, talk to your health care provider.
5. MISSING PILLS CAN ALSO CAUSE SPOTTING OR LIGHT BLEEDING, even when you make up these missed pills.
  On the days you take 2 pills to make up for missed pills, you could also feel a little sick to your stomach.
6. IF YOU VOMIT (within 4 hours after you take your pill), you should follow the instructions for WHAT TO DO IF YOU MISS PILLS. IF YOU HAVE DIARRHEA or IF YOU TAKE SOME MEDICINES, including some antibiotics, your pills may not work as well.
  Use a back-up nonhormonal method (such as condoms and/or spermicide) until you check with your health care professional.
7. IF YOU HAVE TROUBLE REMEMBERING TO TAKE LEVONORGESTREL AND ETHINYL ESTRADIOL, talk to your health care professional about how to make pill-taking easier or about using another method of birth control.
8. IF YOU HAVE ANY QUESTIONS OR ARE UNSURE ABOUT THE INFORMATION IN THIS LEAFLET, call your health care professional.

BEFORE YOU START TAKING LEVONORGESTREL AND ETHINYL ESTRADIOL

1. DECIDE WHAT TIME OF DAY YOU WANT TO TAKE YOUR PILL. It is important to take your pill at the SAME TIME every day.
2. LOOK AT YOUR LEVONORGESTREL AND ETHINYL ESTRADIOL BLISTER. The pill pack has 28 “active” brownish peach to light brown pills (with hormones).
3. Locate the top row of the blister.
4. Pick the day label strip that starts with the first day of your period (this is the day you start bleeding or spotting, even if it is almost midnight when the bleeding begins).
5. Place the day label strip on the tablet blister over the area that has the days of the week (starting with Sunday) imprinted in the plastic.

1. When it comes time to take levonorgestrel and ethinyl estradiol, you will take each pill until the blister is empty.
2. BE SURE YOU HAVE READY AT ALL TIMES:
  ANOTHER KIND OF NONHORMONAL BIRTH CONTROL (such as condoms and/or spermicide) to use as a back-up in case you miss pills.
  AN EXTRA, FULL PILL PACK.

WHEN TO START THE FIRST PACK OF LEVONORGESTREL AND ETHINYL ESTRADIOL

Day 1 Start

1. Take the first “active” brownish peach to light brown pill of the first pack during the first 24 hours of your period.
2. You will not need to use a back-up nonhormonal method of birth control, since you are starting the pill at the beginning of your period.

WHAT TO DO DURING THE MONTH

1. TAKE ONE PILL AT THE SAME TIME EVERY DAY UNTIL THE BLISTER PACK IS EMPTY. Do not skip pills even if you are spotting or bleeding or feel sick to your stomach (nausea).
  Do not skip pills even if you do not have sex very often.
2. WHEN YOU FINISH A PACK
  Start the next pack on the day after your last pill. Do not wait any days between packs.

IF YOU SWITCH FROM ANOTHER BRAND OF COMBINATION PILLS:

When switching from a 21 pill pack: Start levonorgestrel and ethinyl estradiol on the first day of your period (withdrawal bleed). Be sure that no more than 7 days pass between the last day of your 21-day pack and your first levonorgestrel and ethinyl estradiol pill.

When switching from a 28 pill pack (21 active and 7 inactive pills, or 24 active and 4 inactive pills): Start levonorgestrel and ethinyl estradiol on the first day of your period (withdrawal bleed). Be sure that no more than 7 days pass after the last active pill and your first levonorgestrel and ethinyl estradiol pill.

IF YOU SWITCH FROM ANOTHER TYPE OF BIRTH CONTROL

When switching from other types of birth control such as pills containing only a progestin (progestin only pill or POP), an injection, or an implant, your health care professional will provide you with instructions for when to start levonorgestrel and ethinyl estradiol.

WHAT TO DO IF YOU MISS PILLS

Combination oral contraceptives may not be as effective if you miss pills. Instructions for what to do if you miss pills are provided in the following table.

# of pills missed in a row | What to do when you miss a pill(s)
1 missed pill | • Take the missed pill as soon as you remember. THEN • Take the next pill at your regular time. This means you may take 2 pills in 1 day. • You COULD BECOME PREGNANT if you have sex during the 7 days after you restart your pills. You MUST use a nonhormonal birth-control method (such as condoms and/or spermicide) as a back-up for those 7 days.
2 missed pills and remembered on the day of the second missed pill | • Take 2 missed pills on the day you remember. The following day you are back on schedule to take 1 pill a day. For example, you take your pills in the morning and you missed 1 pill on Monday and 1 on Tuesday. On Tuesday evening you remembered that you missed your Monday and Tuesday pills. You take the 2 missed pills on Tuesday evening and on Wednesday morning you're back on schedule and you take 1 pill. • You COULD BECOME PREGNANT if you have sex during the 7 days after you restart your pills. You MUST use a nonhormonal birth-control method (such as condoms and/or spermicide) as a back-up for those 7 days.
2 missed pills and remembered on the day after the second pill is missed | • Take 2 missed pills on the day you remember. The next day you take 2 pills. The following day you are back on schedule to take your pills. For example, you take your pills in the morning and you missed 1 pill on Monday and 1 on Tuesday. On Wednesday morning you remembered that you missed your Monday and Tuesday pills. You take the 2 missed pills on Wednesday morning and 2 pills on Thursday morning. On Friday morning you're back on schedule and you take 1 pill. • You COULD BECOME PREGNANT if you have sex during the 7 days after you restart your pills. You MUST use a nonhormonal birth-control method (such as condoms and/or spermicide) as a back-up for those 7 days.
3 or more missed pills | • Contact your health care professional for further advice. Keep taking one pill every day until you reach your health care professional. Do not take the missed pills. • You COULD BECOME PREGNANT if you have sex during the 7 days after you restart your pills. You MUST use a nonhormonal birth-control method (such as condoms and/or spermicide) as a back-up for those 7 days.

FINALLY, IF YOU ARE STILL NOT SURE WHAT TO DO ABOUT THE PILLS YOU HAVE MISSED

Use a BACK-UP NONHORMONAL BIRTH-CONTROL METHOD anytime you have sex. KEEP TAKING ONE PILL EACH DAY until you can reach your health care professional.

PREGNANCY DUE TO PILL FAILURE

The incidence of pill failure resulting in pregnancy is approximately 1-2% per year (1 to 2 pregnancies per 100 women per year of use) if taken every day as directed, but the average failure rate is approximately 5% per year (5 pregnancies per 100 women per year of use) including women who do not always take the pill exactly as directed without missing any pills. If you do become pregnant, the risk to the fetus is minimal, but you should stop taking your pills and discuss the pregnancy with your health care professional.

PREGNANCY AFTER STOPPING THE PILL

If you do not desire pregnancy, you should use another method of birth-control immediately after stopping levonorgestrel and ethinyl estradiol. A pregnancy can occur within days after stopping levonorgestrel and ethinyl estradiol.

There does not appear to be any increase in birth defects in newborn babies when pregnancy occurs soon after stopping the pill.

There may be some delay in becoming pregnant after you stop using oral contraceptives, especially if you had irregular menstrual cycles before you used oral contraceptives. It may be advisable to postpone conception until you begin menstruating regularly once you have stopped taking the pill and desire pregnancy.

OVERDOSAGE

Overdosage may cause nausea, vomiting, breast tenderness, dizziness, abdominal pain, and fatigue/drowsiness. Withdrawal bleeding may occur in females. In case of overdosage, contact your health care professional or pharmacist.

OTHER INFORMATION

Your health care professional will take a medical and family history before prescribing oral contraceptives and will examine you. The physical examination may be delayed to another time if you request it and the health care professional believes that it is appropriate to postpone it. You should be reexamined at least once a year. Be sure to inform your health care professional if there is a family history of any of the conditions listed previously in this leaflet. Be sure to keep all appointments with your health care professional, because this is a time to determine if there are early signs of side effects of oral contraceptive use.

Do not use the drug for any condition other than the one for which it was prescribed. This drug has been prescribed specifically for you; do not give it to others who may want birth-control pills.

HEALTH BENEFITS FROM ORAL CONTRACEPTIVES

In addition to preventing pregnancy, some information suggests that the use of oral contraceptives provide certain other benefits. The benefits are:

1. Decreased blood loss, and less iron may be lost. Therefore, anemia due to iron deficiency is less likely to occur.
2. Pain or other cycle-related symptoms may occur less frequently.
3. Ovarian cysts may occur less frequently.
4. Ectopic (tubal) pregnancy may occur less frequently.
5. Noncancerous cysts or lumps in the breast may occur less frequently.
6. Acute pelvic inflammatory disease may occur less frequently.
7. Oral contraceptive use may provide some protection against developing two forms of cancer: cancer of the ovaries and cancer of the lining of the uterus.

If you want more information about birth-control pills, ask your health care professional or pharmacist. They have a more technical leaflet called the Professional Labeling which you may wish to read.

Distributed by:

Glenmark Pharmaceuticals Inc., USA
Elmwood Park, NJ 07407

Questions? 1 (888) 721-7115
www.glenmarkpharma-us.com

June 2025

Package/Label Display Panel - Carton

NDC 68462-637-29

Levonorgestrel and Ethinyl Estradiol Tablets USP
0.09 mg/0.02 mg

Package/Label Display Panel - Pouch

NDC 68462-637-84